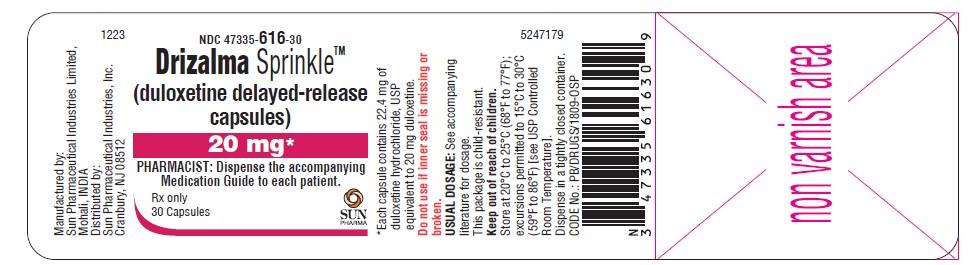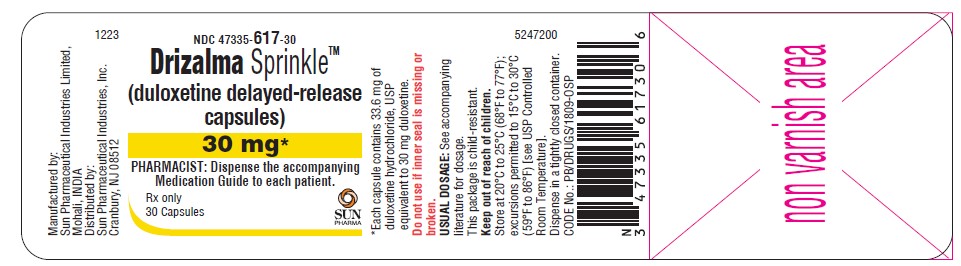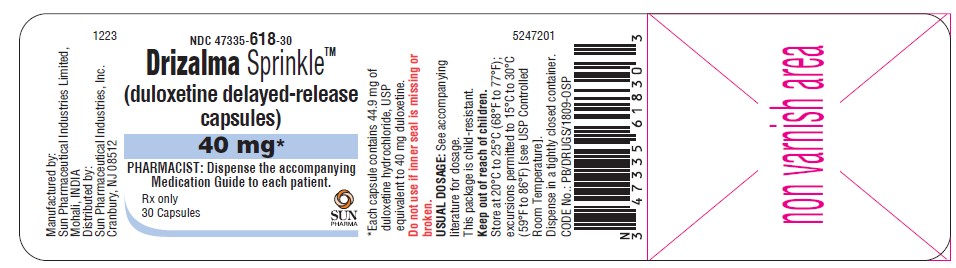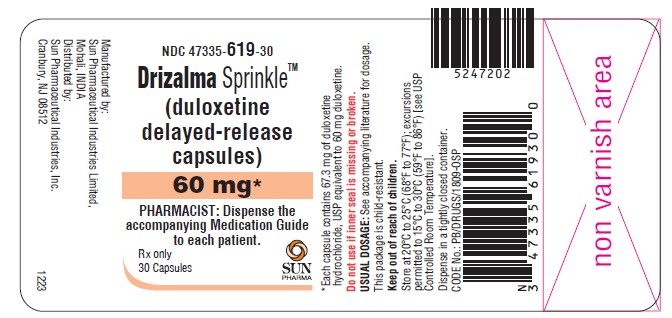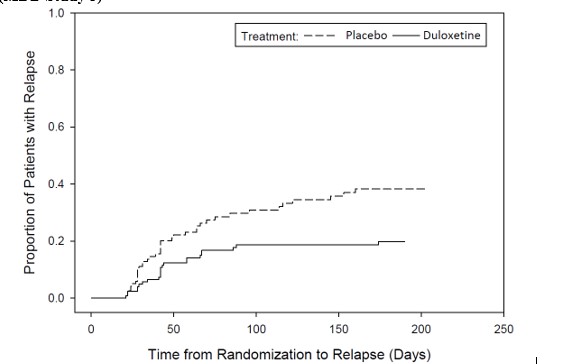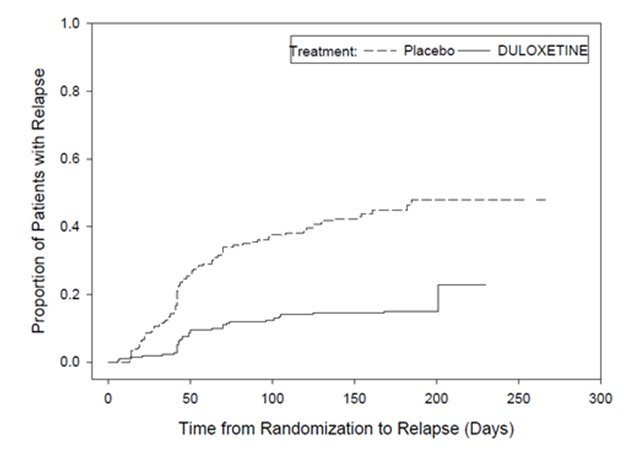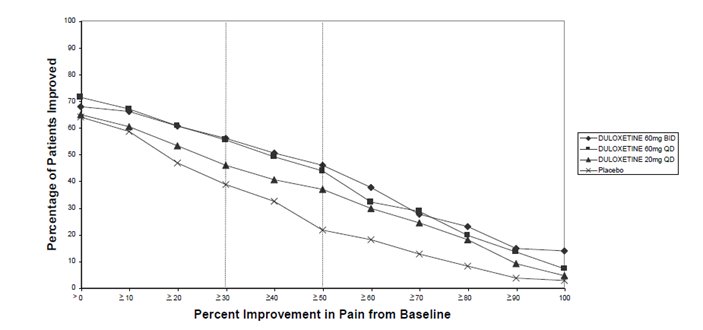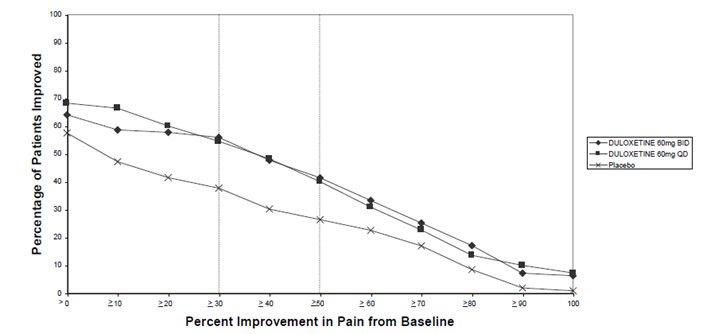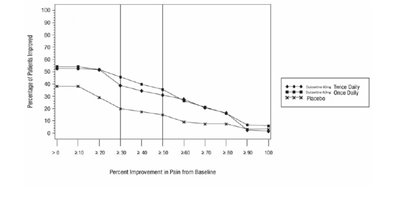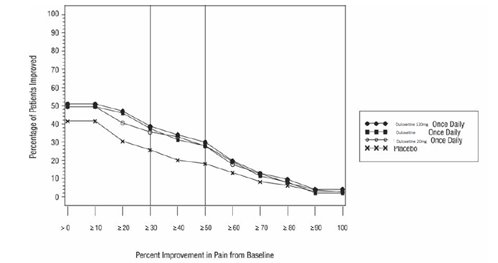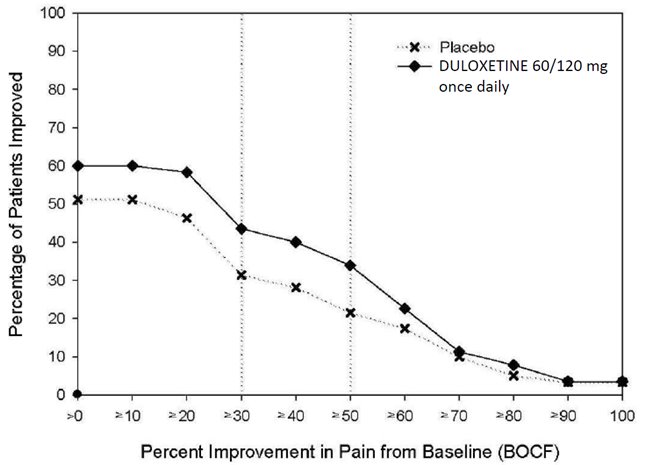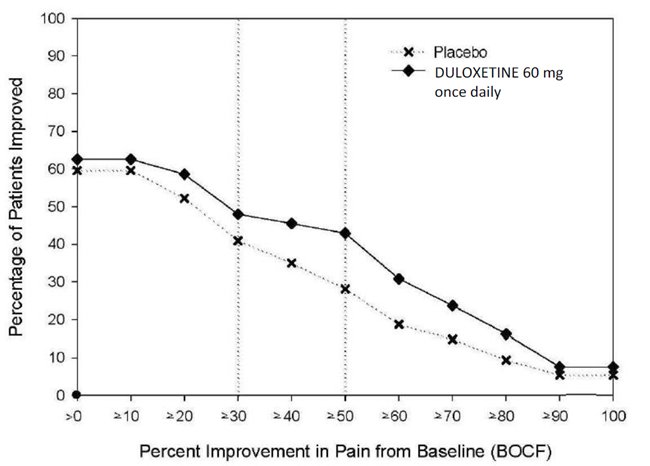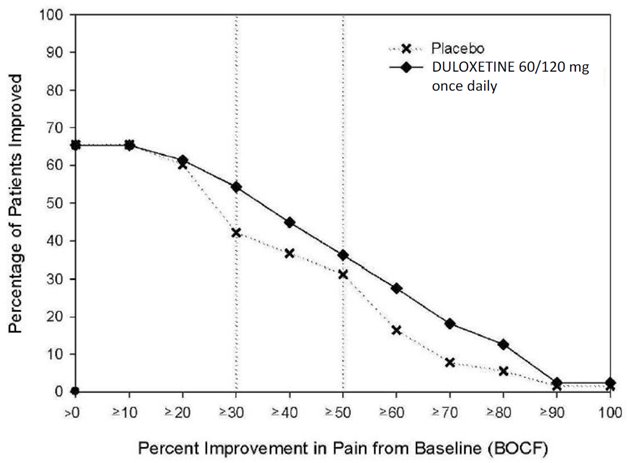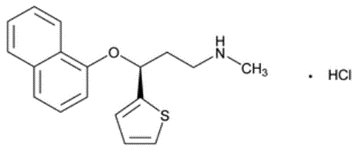 DRUG LABEL: DRIZALMA SPRINKLE
NDC: 47335-616 | Form: CAPSULE, DELAYED RELEASE
Manufacturer: SUN PHARMACEUTICAL INDUSTRIES, INC.
Category: prescription | Type: HUMAN PRESCRIPTION DRUG LABEL
Date: 20240514

ACTIVE INGREDIENTS: DULOXETINE HYDROCHLORIDE 20 mg/1 1
INACTIVE INGREDIENTS: TALC; TITANIUM DIOXIDE; D&C YELLOW NO. 10; FD&C BLUE NO. 1; FD&C RED NO. 40; GELATIN, UNSPECIFIED; SODIUM LAURYL SULFATE; FERROSOFERRIC OXIDE; SHELLAC; POLYETHYLENE GLYCOL, UNSPECIFIED; HYPROMELLOSE, UNSPECIFIED; HYPROMELLOSE PHTHALATE (24% PHTHALATE, 55 CST); STARCH, CORN; TRIETHYL CITRATE; PROPYLENE GLYCOL; SUCROSE; ASCORBIC ACID; AMMONIA

HIGHLIGHTS OF PRESCRIBING INFORMATION

These highlights do not include all the information needed to use DRIZALMA SPRINKLE safely and effectively. See full prescribing information for DRIZALMA SPRINKLE.
DRIZALMA SPRINKLE™ (duloxetine delayed-release capsules), for oral use.
Initial U.S. Approval: 2004

RECENT MAJOR CHANGES

Warnings and Precautions (5.4, 5.5) 08/2023

WARNING: SUICIDAL THOUGHTS AND BEHAVIORS

See full prescribing information for complete boxed warning.

•Increased risk of suicidal thinking and behavior in pediatric and young adult patients taking antidepressants (5.1)

•Closely monitor all antidepressant-treated patients for clinical worsening and emergence of suicidal thoughts and behaviors (5.1)

1 INDICATIONS AND USAGE

DRIZALMA SPRINKLE is a serotonin and norepinephrine reuptake inhibitor (SNRI) indicated for the treatment of following conditions:
• Major Depressive Disorder (MDD) in adults (1)
• Generalized Anxiety Disorder (GAD) in adults and pediatric patients ages 7 years of age and older (1)
• Diabetic Peripheral Neuropathic Pain (DPNP) in adults (1)
• Fibromyalgia (FM) in adults (1)
• Chronic Musculoskeletal Pain in adults (1)

2 DOSAGE AND ADMINISTRATION

- Take DRIZALMA SPRINKLE with or without food (2.1)
- DRIZALMA SPRINKLE may be: swallowed whole (do not crush or chew capsule); opened and sprinkled over applesauce; or administered via nasogastric tube (2.1)
- Take a missed dose as soon as it is remembered. Do not take two doses of DRIZALMA SPRINKLE at the same time (2.1)

Indication | Starting Dose | Target Dose | Maximum Dose
MDD (2.2); Adults | 40 mg/day to; 60 mg/day | Acute Treatment: 40 mg/day (20 mg twice daily) to 60 mg/day (once daily or as 30 mg twice daily); Maintenance Treatment: 60 mg/day | 120 mg/day
GAD (2.3)
Adults | 60 mg/day | 60 mg/day (once daily) | 120 mg/day
Geriatric | 30 mg/day | 60 mg/day (once daily) | 120 mg/day
Pediatrics (7 to 17 years of age) | 30 mg/day | 30 to 60 mg/day (once daily) | 120 mg/day
DPNP (2.4) | 60 mg/day | 60 mg/day (once daily) | 60 mg/day
FM (2.5); Adults | 30 mg/day | 60 mg/day (once daily) | 60 mg/day
Chronic Musculoskeletal Pain; (2.6) Adults | 30 mg/day | 60 mg/day (once daily) | 60 mg/day

- There is no evidence that doses greater than 60 mg/day confers additional benefit, while some adverse reactions were observed to be dose-dependent (2)
- Discontinuing DRIZALMA SPRINKLE: Gradually reduce dosage to avoid discontinuation symptoms (2.8, 5.7)

3 DOSAGE FORMS AND STRENGTHS

Delayed-release capsules: 20 mg, 30 mg, 40 mg, and 60 mg (3)

4 CONTRAINDICATIONS

- Serotonin Syndrome and MAOIs: Do not use MAOIs intended to treat psychiatric disorders with DRIZALMA SPRINKLE or within 5 days of stopping treatment with DRIZALMA SPRINKLE. Do not use DRIZALMA SPRINKLE within 14 days of stopping an MAOI intended to treat psychiatric disorders. In addition, do not start DRIZALMA SPRINKLE in a patient who is being treated with linezolid or intravenous methylene blue (4)

5 WARNINGS AND PRECAUTIONS

- Hepatotoxicity: Hepatic failure, sometimes fatal, has been reported. Discontinue DRIZALMA SPRINKLE in patients who develop jaundice or other evidence of clinically significant liver dysfunction and should not be resumed unless another cause can be established. Avoid use in patients with substantial alcohol use or evidence of chronic liver disease (5.2)
  - Orthostatic Hypotension, Falls and Syncope: Consider dosage reduction or discontinuation if these events occur (5.3)
  - Serotonin Syndrome: Increased risk when co-administered with other serotonergic agents, but also when taken alone. If it occurs, discontinue DRIZALMA SPRINKLE and serotonergic agents and initiate supportive treatment (5.4)
  - Increased Risk of Bleeding: May increase the risk of bleeding events. Concomitant use of antiplatelet drugs and anticoagulants may increase this risk (5.5, 7, 8.1)
  - Severe Skin Reactions: Severe skin reactions, including erythema multiforme and Stevens-Johnson Syndrome (SJS), can occur with duloxetine. Discontinue at the first appearance of blisters, peeling rash, mucosal erosions, or any other sign of hypersensitivity if no other etiology can be identified (5.6)
  - Discontinuation Syndrome: Taper dose when possible and monitor for discontinuation symptoms (5.7)
  - Activation of Mania or Hypomania: Prior to initiating, screen patients for personal or family history of bipolar disorder, mania, or hypomania (5.8)
  - Angle-Closure Glaucoma: Has occurred in patients with untreated anatomically narrow angles treated with antidepressants (5.9)
  - Seizures: Prescribe with care in patients with a history of seizure disorder (5.10)
  - Blood Pressure Increases: Monitor blood pressure prior to initiating treatment and periodically throughout treatment (5.11)
  - Inhibitors of CYP1A2 or Thioridazine: Avoid co-administration with DRIZALMA SPRINKLE (5.12)
    - Hyponatremia: Can occur in association with SIADH; consider discontinuation (5.13)
    - Glucose Control in Diabetes: In DPNP patients, increase in fasting blood glucose, and HbA1c have been observed (5.14)
    - Conditions that Slow Gastric Emptying: Use cautiously in these patients (5.14)
    - Sexual Dysfunction: DRIZALMA SPRINKLE may cause symptoms of sexual dysfunction (5.16)

6 ADVERSE REACTIONS

Most common adverse reactions (≥5% and at least twice the incidence of placebo-treated patients): (6.1)

Adults: nausea, dry mouth, somnolence, constipation, decreased appetite, and hyperhidrosis

Pediatric Patients: nausea, diarrhea, decreased weight

To report SUSPECTED ADVERSE REACTIONS, contact Sun Pharmaceutical Industries, Inc. at 1-800-818-4555 or FDA at 1-800-FDA-1088 or www.fda.gov/medwatch.

7 DRUG INTERACTIONS

- Potent CYP1A2 Inhibitors: Avoid concomitant use (2.6, 7)
- CYP2D6 Substrates: Consider dose reduction with concomitant use (7)

8 USE IN SPECIFIC POPULATIONS

- Pregnancy: Third trimester use may increase risk for symptoms of poor adaptation (respiratory distress, temperature instability, feeding difficulty, hypotonia, tremor, irritability) in the neonate (8.1)
- Hepatic Impairment: Avoid use in patients with chronic liver disease or cirrhosis (5.14)
- Renal Impairment: Avoid use in patients with severe renal impairment, GFR <30 mL/minute (5.14)

FULL PRESCRIBING INFORMATION

WARNING: SUICIDAL THOUGHTS AND BEHAVIORS

Antidepressants increased the risk of suicidal thoughts and behavior in pediatric and young adult patients in short-term studies.

Closely monitor all antidepressant-treated patients for clinical worsening, and for emergence of suicidal thoughts and behaviors [see Warnings and Precautions (5.1)].

1 INDICATIONS AND USAGE

DRIZALMA SPRINKLE is indicated for the treatment of:

- Major Depressive Disorder in adults
- Generalized Anxiety Disorder in adults and pediatric patients 7 years of age and older
- Diabetic Peripheral Neuropathy in adults
- Fibromyalgia in adults
- Chronic Musculoskeletal Pain in adults

Additional pediatric use information is approved for Eli Lilly and Company, Inc.’s CYMBALTA (duloxetine delayed-release capsules). However, due to Eli Lilly and Company Inc.’s marketing exclusivity rights, this drug product is not labeled with that pediatric information.

2 DOSAGE AND ADMINISTRATION

2.1 Important Administration Instructions

Administer DRIZALMA SPRINKLE with or without food. Swallow DRIZALMA SPRINKLE whole (do not chew or crush the capsule). For patients unable to swallow an intact capsule, refer to the alternative administration instructions below.

Directions for use with applesauce

For patients with swallowing difficulty, DRIZALMA SPRINKLE can be opened and the contents sprinkled over applesauce. The contents of the capsules should be swallowed along with a small amount (tablespoonful) of applesauce. The drug/food mixture should be swallowed immediately and not stored for future use.

Nasogastric tube administration

Open and add contents of capsule to an all plastic catheter tip syringe and add 50 mL of water. Gently shake the syringe for approximately 10 seconds. Promptly deliver through a 12 French or larger nasogastric tube. Ensure no pellets are left in the syringe. Rinse with additional water (about 15 mL) if needed.

If a dose of DRIZALMA SPRINKLE is missed, take the missed dose as soon as it is remembered. If it is almost time for the next dose, skip the missed dose and take the next dose at the regular time. Do not take two doses of DRIZALMA SPRINKLE at the same time.

2.2 Dosage for Treatment of Major Depressive Disorder in Adults

The recommended starting dosage in adults with MDD is 40 mg per day (given as 20 mg twice daily) to 60 mg per day (given either once daily or as 30 mg twice daily). For some patients, it may be desirable to start at 30 mg once daily for 1 week, to allow patients to adjust to DRIZALMA SPRINKLE before increasing to 60 mg once daily. While a 120 mg per day dose was shown to be effective, there is no evidence that doses greater than 60 mg per day confer any additional benefits. Periodically reassess to determine the need for maintenance treatment and the appropriate dosage for such treatment [see Clinical Studies (14.1)].

2.3 Dosage for Treatment of Generalized Anxiety Disorder

Recommended Dosage in Adults Less than 65 Years of Age

For most adults less than 65 years of age with GAD, initiate DRIZALMA SPRINKLE 60 mg once daily. For some patients, it may be desirable to start at 30 mg once daily for 1 week, to allow patients to adjust to DRIZALMA SPRINKLE before increasing to 60 mg once daily. While a 120 mg once daily dosage was shown to be effective, there is no evidence that doses greater than 60 mg per day confer additional benefit. Nevertheless, if a decision is made to increase the dosage beyond 60 mg once daily, increase dosage in increments of 30 mg once daily. The safety of doses above 120 mg once daily has not been adequately evaluated. Periodically reassess to determine the continued need for maintenance treatment and the appropriate dosage for such treatment.

Recommended Dosage in Geriatric Patients

In geriatric patients with GAD, initiate DRIZALMA SPRINKLE at a dosage of 30 mg once daily for 2 weeks before considering an increase to the target dose of 60 mg per day. Thereafter, patients may benefit from doses above 60 mg once daily. If a decision is made to increase the dose beyond 60 mg once daily, increase dose in increments of 30 mg once daily. The maximum dose studied was 120 mg per day.

Recommended Dosage in Pediatric Patients 7 to 17 Years of Age

Initiate DRIZALMA SPRINKLE in pediatric patients 7 to 17 years of age with GAD at a dosage of 30 mg once daily for 2 weeks before considering an increase to 60 mg once daily. The recommended dosage range is 30 to 60 mg once daily. Some patients may benefit from dosages above 60 mg once daily. If a decision is made to increase the dose beyond 60 mg once daily, increase dosage in increments of 30 mg once daily. The maximum dose studied was 120 mg per day.

2.4 Dosage for Treatment of Diabetic Peripheral Neuropathic Pain in Adults

Administer DRIZALMA SPRINKLE 60 mg once daily in adults with diabetic peripheral neuropathic pain. There is no evidence that doses higher than 60 mg once daily confer additional significant benefit and the higher dosage is clearly less well tolerated. For patients for whom tolerability is a concern, a lower starting dose may be considered.

Since diabetes is frequently complicated by renal disease, consider a lower starting dosage and gradual increase in dosage for patients with renal impairment [see Dosage and Administration (2.8) and Use in Specific Populations (8.10)].

2.5 Dosage for Treatment of Fibromyalgia in Adults

Recommended Dosage in Adults

The recommended DRIZALMA SPRINKLE dosage is 60 mg once daily in adults with fibromyalgia. Begin treatment at 30 mg once daily for 1 week, to allow patients to adjust to DRIZALMA SPRINKLE before increasing to 60 mg once daily. Some patients may respond to the starting dosage. There is no evidence that dosages greater than 60 mg/day confer additional benefit, even in patients who do not respond to a 60 mg/day dosage, and higher dosages were associated with a higher rate of adverse reactions.

Additional pediatric use information is approved for Eli Lilly and Company, Inc.’s CYMBALTA (duloxetine delayed-release capsules). However, due to Eli Lilly and Company Inc.’s marketing exclusivity rights, this drug product is not labeled with that pediatric information.

2.6 Dosage for Treatment of Chronic Musculoskeletal Pain in Adults

The recommended DRIZALMA SPRINKLE dosage is 60 mg once daily in adults with chronic musculoskeletal pain. Begin treatment at 30 mg once daily for one week, to allow patients to adjust to DRIZALMA SPRINKLE before increasing to 60 mg once daily. There is no evidence that higher dosage confer additional benefit, even in patients who do not respond to a 60 mg once daily dosage, and higher dosages are associated with a higher rate of adverse reactions [see Clinical Studies (14.5)].

2.7 Dosage Recommendations for Concomitant Use with Potent CYP1A2 Inhibitors

Coadministration with potent CYP1A2 Inhibitors: Avoid concomitant use of DRIZALMA SPRINKLE with potent CYP1A2 inhibitors.

2.8 Dosage in Patients with Hepatic Impairment or Severe Renal Impairment

Avoid use in patients with chronic liver disease or cirrhosis [see Warnings and Precautions (5.14) and Use in Specific Populations (8.9)].

Avoid use in patients with severe renal impairment, GFR <30 mL/minute [see Warnings and Precautions (5.14) and Use in Specific Populations (8.10)].

2.9 Screen for Bipolar Disorder Prior to Starting DRIZALMA SPRINKLE

Prior to initiating treatment with DRIZALMA SPRINKLE or another antidepressant, screen patients for a personal or family history of bipolar disorder, mania, or hypomania [see Warnings and Precautions (5.8)].

2.10 Discontinuing DRIZALMA SPRINKLE

Adverse reactions may occur upon discontinuation of DRIZALMA SPRINKLE [see Warnings and Precautions (5.7)]. Gradually reduce the dosage rather than stopping DRIZALMA SPRINKLE abruptly whenever possible [see Warnings and Precautions (5.7)].

2.11 Switching a Patient to or from a Monoamine Oxidase Inhibitor (MAOI) Intended to Treat Psychiatric Disorders

At least 14 days should elapse between discontinuation of an MAOI intended to treat psychiatric disorders and initiation of therapy with DRIZALMA SPRINKLE. Conversely, at least 5 days should be allowed after stopping DRIZALMA SPRINKLE before starting an MAOI intended to treat psychiatric disorders [see Contraindications (4).

2.12 Use of DRIZALMA SPRINKLE with Other MAOIs such as Linezolid or Methylene Blue

Do not start DRIZALMA SPRINKLE in a patient who is being treated with linezolid or intravenous methylene blue because there is an increased risk of serotonin syndrome. In a patient who requires more urgent treatment of a psychiatric condition, other interventions, including hospitalization, should be considered [see Contraindications (4)].

In some cases, a patient already receiving DRIZALMA SPRINKLE therapy may require urgent treatment with linezolid or intravenous methylene blue. If acceptable alternatives to linezolid or intravenous methylene blue treatment are not available and the potential benefits of linezolid or intravenous methylene blue treatment are judged to outweigh the risks of serotonin syndrome in a particular patient, DRIZALMA SPRINKLE should be stopped promptly, and linezolid or intravenous methylene blue can be administered. The patient should be monitored for symptoms of serotonin syndrome for 5 days or until 24 hours after the last dose of linezolid or intravenous methylene blue, whichever comes first. Therapy with DRIZALMA SPRINKLE may be resumed 24 hours after the last dose of linezolid or intravenous methylene blue [see Warnings and Precautions (5.4)].

The risk of administering methylene blue by non-intravenous routes (such as oral tablets or by local injection) or in intravenous doses much lower than 1 mg/kg with DRIZALMA SPRINKLE is unclear. The clinician should, nevertheless, be aware of the possibility of emergent symptoms of serotonin syndrome with such use [see Warnings and Precautions (5.4)].

3 DOSAGE FORMS AND STRENGTHS

20 mg: hard gelatin capsules with green cap imprinted with “RG53” and green body imprinted with “RG53” containing off-white to pale-yellow colored pellets. Each capsule contains 22.4 mg of duloxetine hydrochloride, USP equivalent to 20 mg duloxetine.

30 mg: hard gelatin capsules with blue cap imprinted with “RG54” and white body imprinted with “RG54” containing off-white to pale-yellow colored pellets. Each capsule contains 33.6 mg of duloxetine hydrochloride, USP equivalent to 30 mg duloxetine.

40 mg: hard gelatin capsules with white cap imprinted with “RL85” and white body imprinted with “RL 85” containing off-white to pale-yellow colored pellets. Each capsule contains 44.9 mg of duloxetine hydrochloride, USP equivalent to 40 mg duloxetine.

60 mg: hard gelatin capsules with blue cap imprinted with “RG55” and green body imprinted with “RG55” containing off-white to pale-yellow colored pellets. Each capsule contains 67.3 mg of duloxetine hydrochloride, USP equivalent to 60 mg duloxetine.

4 CONTRAINDICATIONS

The use of MAOIs intended to treat psychiatric disorders with DRIZALMA SPRINKLE, or within 5 days of stopping treatment with DRIZALMA SPRINKLE, are contraindicated because of an increased risk of serotonin syndrome. The use of DRIZALMA SPRINKLE within 14 days of stopping an MAOI intended to treat psychiatric disorders is contraindicated [see Dosage and Administration (2.10), Warnings and Precautions (5.4), Drug Interactions (7)].

Starting DRIZALMA SPRINKLE in a patient who is being treated with MAOIs such as linezolid or intravenous methylene blue is contraindicated because of an increased risk of serotonin syndrome [see Warnings and Precautions (5.4)].

5 WARNINGS AND PRECAUTIONS

5.1 Suicidal Thoughts and Behaviors in Adolescents and Young Adults

In pooled analyses of placebo-controlled trials of antidepressant drugs (SSRIs and other antidepressant classes) that included approximately 77,000 adult patients and 4,500 pediatric patients, the incidence of suicidal thoughts and behaviors in the antidepressant-treated patients age 24 years and younger was greater than in placebo-treated patients. There was considerable variation in risk of suicidal thoughts and behaviors among drugs, but there was an increased risk identified in young patients for most drugs studied. There were differences in absolute risk of suicidal thoughts and behaviors across the different indications, with the highest incidence in MDD. The drug-placebo differences in the number of cases of suicidal thoughts and behaviors per 1000 patients treated are provided in Table 1.Table 1: Risk Differences of the Number of Patients of Suicidal Thoughts and Behavior in the Pooled Placebo-Controlled Trials of Antidepressants in Pediatric and Adult Patients

Age Range | Drug-Placebo Difference in Number of Patients of Suicidal Thoughts or Behaviors per 1000 Patients Treated
 | Increases Compared to Placebo
<18 | 14 additional patients
18 to 24 | 5 additional patients
 | Decreases Compared to Placebo
25 to 64 | 1 fewer patients
≥65 | 6 fewer patients

It is unknown whether the risk of suicidal thoughts and behaviors in children, adolescents, and young adults extends to longer-term use, i.e., beyond four months. However, there is substantial evidence from placebo-controlled maintenance trials in adults with MDD that antidepressants delay the recurrence of depression and that depression itself is a risk factor for suicidal thoughts and behaviors. Monitor all antidepressant-treated patients for any indication for clinical worsening and emergence of suicidal thoughts and behaviors, especially during the initial few months of drug therapy, and at times of dosage changes. Counsel family members or caregivers of patients to monitor for changes in behavior and to alert the healthcare provider. Consider changing the therapeutic regimen, including possibly discontinuing DRIZALMA SPRINKLE, in patients whose depression is persistently worse, or who are experiencing emergent suicidal thoughts or behaviors.

5.2 Hepatotoxicity

There have been reports of hepatic failure, sometimes fatal, in patients treated with duloxetine delayed-release capsules. These cases have presented as hepatitis with abdominal pain, hepatomegaly, and elevation of transaminase levels to more than twenty times the upper limit of normal (ULN) with or without jaundice, reflecting a mixed or hepatocellular pattern of liver injury. Discontinue DRIZALMA SPRINKLE in patients who develop jaundice or other evidence of clinically significant liver dysfunction and do not resume unless another cause can be established.

Cases of cholestatic jaundice with minimal elevation of transaminase levels have also been reported. Other post-marketing reports indicate that elevated transaminases, bilirubin, and alkaline phosphatase have occurred in patients with chronic liver disease or cirrhosis.

Duloxetine delayed-release capsules increased the risk of elevation of serum transaminase levels in development program clinical trials. Liver transaminase elevations resulted in the discontinuation of 0.3% (92/34,756) of duloxetine delayed-release capsules-treated patients. In most patients, the median time to detection of the transaminase elevation was about two months. In adult placebo-controlled trials in any indication, for patients with normal and abnormal baseline ALT values, elevation of ALT > 3 times the upper limit of normal occurred in 1.25% (144/11,496) of duloxetine delayed-release capsules-treated patients compared to 0.45% (39/8716) of placebo- treated patients. In adult placebo-controlled studies with duloxetine delayed-release capsules using a fixed dose design, there was evidence of a dose response relationship for ALT and AST elevation of >3 times the ULN and >5 times the ULN, respectively.

Because it is possible that duloxetine and alcohol may interact to cause liver injury or that duloxetine may aggravate pre-existing liver disease, DRIZALMA SPRINKLE should not be prescribed to patients with substantial alcohol use or evidence of chronic liver disease.

5.3 Orthostatic Hypotension, Falls and Syncope

Orthostatic hypotension, falls, and syncope have been reported in patients treated with the recommended duloxetine delayed-release capsules dosage. Syncope and orthostatic hypotension tend to occur within the first week of therapy but can occur at any time during DRIZALMA SPRINKLE treatment, particularly after dose increases. The risk of falling appears to be related to the degree of orthostatic decrease in blood pressure (BP) as well as other factors that may increase the underlying risk of falls.

In an analysis of patients from all placebo-controlled trials, patients treated with duloxetine delayed-release capsules reported a higher rate of falls compared to patients treated with placebo. Risk appears to be related to the presence of orthostatic decrease in BP. The risk of BP decreases may be greater in patients taking concomitant medications that induce orthostatic hypotension (such as anti-hypertensives) or are potent CYP1A2 inhibitors [see Warnings and Precautions (5.12) and Drug Interactions (7.1)] and in patients taking DRIZALMA SPRINKLE at doses above 60 mg daily. Consider dose reduction or discontinuation of DRIZALMA SPRINKLE in patients who experience symptomatic orthostatic hypotension, falls and/or syncope during DRIZALMA SPRINKLE therapy.

Risk of falling also appeared to be proportional to a patient’s underlying risk for falls and appeared to increase steadily with age. As geriatric patients tend to have a higher underlying risk for falls due to a higher prevalence of risk factors such as use of multiple medications, medical comorbidities and gait disturbances, the impact of increasing age by itself is unclear. Falls with serious consequences including fractures and hospitalizations have been reported with duloxetine delayed-release capsules use [see Adverse Reactions (6.1)].

5.4 Serotonin Syndrome

Serotonin-norepinephrine reuptake inhibitors (SNRIs) and selective-serotonin reuptake inhibitors (SSRIs), including DRIZALMA SPRINKLE, can precipitate serotonin syndrome, a potentially life-threatening condition. The risk is increased with concomitant use of other serotonergic drugs (including triptans, tricyclic antidepressants, fentanyl, lithium, tramadol, meperidine, methadone, tryptophan, buspirone, amphetamines, and St. John’s Wort) and with drugs that impair metabolism of serotonin [see Contraindications (4), Drug Interactions (7)]. Serotonin syndrome can also occur when these drugs are used alone.

Serotonin syndrome symptoms may include mental status changes (e.g., agitation, hallucinations, delirium, and coma), autonomic instability (e.g., tachycardia, labile blood pressure, dizziness, diaphoresis, flushing, hyperthermia), neuromuscular symptoms (e.g., tremor, rigidity, myoclonus, hyperreflexia, incoordination), seizures, and gastrointestinal symptoms (e.g., nausea, vomiting, diarrhea).

The concomitant use of DRIZALMA SPRINKLE with MAOI antidepressant is contraindicated. In addition, do not initiate DRIZALMA SPRINKLE in a patient who is being treated with MAOIs such as linezolid or intravenous methylene blue. No reports involved the administration of methylene blue by other routes (such as oral tablets or local tissue injection). If it is necessary to initiate treatment with an MAOI such as linezolid or intravenous methylene blue in a patient taking DRIZALMA SPRINKLE, discontinue DRIZALMA SPRINKLE before initiating treatment with the MAOI [see Contraindications (4), Drug Interactions (7)].

Monitor all patients taking DRIZALMA SPRINKLE for the emergence of serotonin syndrome. Discontinue treatment with DRIZALMA SPRINKLE capsules immediately if the above symptoms occur and initiate supportive symptomatic treatment. If concomitant use of DRIZALMA SPRINKLE with other serotonergic drugs is clinically warranted, inform patients of the increased risk for serotonin syndrome and monitor for symptoms.

5.5 Increased Risk of Bleeding

Drugs that interfere with serotonin reuptake inhibition, including DRIZALMA SPRINKLE, may increase the risk of bleeding events. Concomitant use of aspirin, non-steroidal anti-inflammatory drugs (NSAIDs), warfarin, and other anti-coagulants may add to this risk. Case reports and epidemiological studies (case-control and cohort design) have demonstrated an association between use of drugs that interfere with serotonin reuptake and the occurrence of gastrointestinal bleeding. A post-marketing study showed a higher incidence of postpartum hemorrhage in mothers taking duloxetine. Other bleeding events related to SSRIs and SNRIs use have ranged from ecchymoses, hematomas, epistaxis, and petechiae to life-threatening hemorrhages.

Inform patients about the increased risk of bleeding associated with the concomitant use of DRIZALMA SPRINKLE and NSAIDs, aspirin, or other drugs that affect coagulation [see Drug Interactions (7.1)].

5.6 Severe Skin Reactions

Severe skin reactions, including erythema multiforme and Stevens-Johnson Syndrome (SJS), can occur with DRIZALMA SPRINKLE. The reporting rate of SJS associated with duloxetine use exceeds the general population background incidence rate for this serious skin reaction (1 to 2 cases per million person years). The reporting rate is generally accepted to be an underestimate due to underreporting.

DRIZALMA SPRINKLE should be discontinued at the first appearance of blisters, peeling rash, mucosal erosions, or any other sign of hypersensitivity if no other etiology can be identified.

5.7 Discontinuation Syndrome

Discontinuation symptoms have been systematically evaluated in patients taking duloxetine. Following abrupt or tapered discontinuation in adult placebo-controlled clinical trials, the following symptoms occurred at 1% or greater and at a significantly higher rate in duloxetine-treated patients compared to those discontinuing from placebo: dizziness, headache, nausea, diarrhea, paresthesia, irritability, vomiting, insomnia, anxiety, hyperhidrosis, and fatigue.

Adverse reactions after discontinuation of serotonergic antidepressants, particularly after abrupt discontinuation, include: nausea, sweating, dysphoric mood, irritability, agitation, dizziness, sensory disturbances (e.g., paresthesias, such as electric shock sensations), tremor, anxiety, confusion, headache, lethargy, emotional lability, insomnia, hypomania, tinnitus, and seizures.

Monitor patients for these symptoms when discontinuing treatment with DRIZALMA SPRINKLE [see Dosage and Administration (2.10)]. A gradual reduction in dosage rather than abrupt cessation is recommended whenever possible. If intolerable symptoms occur following a decrease in the dose or upon discontinuation of treatment, then resuming the previously prescribed dose may be considered. Subsequently, the healthcare provider may continue decreasing the dose but at a more gradual rate [see Dosage and Administration (2.9)].

5.8 Activation of Mania/Hypomania

In patients with bipolar disorder, treating a depressive episode with DRIZALMA SPRINKLE or another antidepressant may precipitate a mixed/manic episode. In controlled clinical trials in adult patients with major depressive disorder, patients with bipolar disorder were generally excluded; however, symptoms of mania or hypomania were reported in 0.1% of patients treated with duloxetine delayed-release capsules. No activation of mania or hypomania was reported in DPNP, GAD, fibromyalgia, or chronic musculoskeletal pain placebo-controlled trials.

Prior to initiating treatment with DRIZALMA SPRINKLE, screen patients for any personal or family history of bipolar disorder, mania, or hypomania.

5.9 Angle-Closure Glaucoma

The pupillary dilation that occurs following use of many antidepressant drugs, including DRIZALMA SPRINKLE, may trigger an angle closure attack in a patient with anatomically narrow angles who does not have a patent iridectomy. Avoid use of antidepressants, including DRIZALMA SPRINKLE, in patients with anatomically narrow angles.

5.10 Seizures

Duloxetine has not been systematically evaluated in patients with a seizure disorder, and such patients were excluded from clinical studies. In adult placebo-controlled clinical trials, seizures/convulsions occurred in 0.02% (3/12,722) of patients treated with duloxetine delayed-release capsules and 0.01% (1/9513) of patients treated with placebo. DRIZALMA SPRINKLE should be prescribed with care in patients with a history of a seizure disorder.

5.11 Increases in Blood Pressure

In adult placebo-controlled clinical trials across the approved adult populations from baseline to endpoint, duloxetine treatment was associated with mean increases of 0.5 mm Hg in systolic blood pressure and 0.8 mm Hg in diastolic blood pressure compared to mean decreases of 0.6 mm Hg systolic and 0.3 mm Hg diastolic in placebo-treated patients. There was no significant difference in the frequency of sustained (3 consecutive visits) elevated blood pressure.

Patients receiving DRIZALMA SPRINKLE should have regular monitoring of blood pressure since increases in blood pressure were observed in clinical studies [see Adverse Reactions (6.1)]. Pre-existing hypertension should be controlled before initiating treatment with DRIZALMA SPRINKLE. Caution should be exercised in treating patients with pre-existing hypertension, cardiovascular, or cerebrovascular conditions that might be compromised by increases in blood pressure.

Sustained blood pressure increases could have adverse consequences. For patients who experience a sustained increase in blood pressure while receiving DRIZALMA SPRINKLE, either dose reduction or discontinuation should be considered [see Adverse Reactions (6.1), Drug Interactions (7.1)]].

5.12 Clinically Important Drug Interactions

Both CYP1A2 and CYP2D6 are responsible for duloxetine metabolism.

Potential for Other Drugs to Affect DRIZALMA SPRINKLE

CYP1A2 Inhibitors – Avoid concomitant use of DRIZALMA SPRINKLE with potent CYP1A2 inhibitors [see Drug Interactions (7.1)].

CYP2D6 Inhibitors - Concomitant use of DRIZALMA SPRINKLE with potent inhibitors of CYP2D6 would be expected to, and does, result in higher concentrations (on average of 60%) of duloxetine [see Drug Interactions (7.1)].

Potential for DRIZALMA SPRINKLE to Affect Other Drugs

Drugs Metabolized by CYP2D6 - Co-administration of DRIZALMA SPRINKLE with drugs that are extensively metabolized by CYP2D6 and that have a narrow therapeutic index, including certain antidepressants (tricyclic antidepressants [TCAs], such as nortriptyline, amitriptyline, and imipramine), phenothiazines and Type 1C antiarrhythmics (e.g., propafenone, flecainide), should be approached with caution. Plasma TCA concentrations may need to be monitored and the dose of the TCA may need to be reduced if a TCA is co-administered with DRIZALMA SPRINKLE. Because of the risk of serious ventricular arrhythmias and sudden death potentially associated with elevated plasma levels of thioridazine, DRIZALMA SPRINKLE and thioridazine should not be co-administered [see Drug Interactions (7.1)].

Other Clinically Important Drug Interactions

Alcohol - Use of DRIZALMA SPRINKLE concomitantly with heavy alcohol intake may be associated with severe liver injury. For this reason, DRIZALMA SPRINKLE should not be prescribed for patients with substantial alcohol use [see Warnings and Precautions (5.2)].

When duloxetine and ethanol were administered several hours apart so that peak concentrations of each would coincide, duloxetine did not increase the impairment of mental and motor skills caused by alcohol.

In the duloxetine clinical trials database, three duloxetine-treated patients had liver injury as manifested by ALT and total bilirubin elevations, with evidence of obstruction. Substantial intercurrent ethanol use was present in each of these cases, and this may have contributed to the abnormalities seen [see Warnings and Precautions (5.2), Drug Interactions (7.1)].

CNS Acting Drugs - Given the primary CNS effects of duloxetine, DRIZALMA SPRINKLE should be used with caution when it is taken in combination with or substituted for other centrally acting drugs, including those with a similar mechanism of action [see Drug Interactions (7.1)].

5.13 Hyponatremia

Hyponatremia may occur as a result of treatment with SSRIs and SNRIs, including DRIZALMA SPRINKLE. In many cases, this hyponatremia appears to be the result of the syndrome of inappropriate antidiuretic hormone secretion (SIADH). Cases with serum sodium lower than 110 mmol/L have been reported. Geriatric patients may be at greater risk of developing hyponatremia with SSRIs and SNRIs. Also, patients taking diuretics or who are otherwise volume depleted may be at greater risk [see Use in Specific Populations (8.5)]. Discontinuation of DRIZALMA SPRINKLE should be considered in patients with symptomatic hyponatremia and appropriate medical intervention should be instituted.

Signs and symptoms of hyponatremia include headache, difficulty concentrating, memory impairment, confusion, weakness, and unsteadiness, which may lead to falls. Signs and symptoms associated with more severe and/or acute cases have been included hallucination, syncope, seizure, coma, respiratory arrest, and death.

5.14 Use in Patients with Concomitant Illness

Clinical experience with duloxetine delayed-release capsules in patients with concomitant systemic illnesses is limited. There is no information on the effect that alterations in gastric motility may have on the stability of DRIZALMA SPRINKLE enteric coating. In extremely acidic conditions, duloxetine, unprotected by the enteric coating, may undergo hydrolysis to form naphthol. Caution is advised in using DRIZALMA SPRINKLE in patients with conditions that may slow gastric emptying (e.g., some diabetics).

DRIZALMA SPRINKLE has not been systematically evaluated in patients with a recent history of myocardial infarction or unstable coronary artery disease. Patients with these diagnoses were generally excluded from clinical studies during the product’s premarketing testing.

Hepatic Impairment

Avoid use in patients with chronic liver disease or cirrhosis [see Dosage and Administration (2.7), Warnings and Precautions (5.2), and Use in Specific Populations (8.9)].

Severe Renal Impairment

Avoid use in patients with severe renal impairment, GFR < 30 mL/minute. Increased plasma concentration of duloxetine, and especially of its metabolites, occur in patients with end-stage renal disease (requiring dialysis) [see Dosage and Administration (2.7) and Use in Specific Populations (8.10)].

Glycemic Control in Patients with Diabetes

As observed in DPNP trials, duloxetine delayed-release capsules treatment worsened glycemic control in some patients with diabetes. In three clinical trials of duloxetine delayed-release capsules for the management of neuropathic pain associated with diabetic peripheral neuropathy [see clinical studies (14.3)], the mean duration of diabetes was approximately 12 years, the mean baseline fasting blood glucose was 176 mg/dL, and the mean baseline hemoglobin A1c (HbA1c) was 7.8%. In the 12 week acute treatment phase of these studies, duloxetine delayed-release capsules was associated with a small increase in mean fasting blood glucose as compared to placebo. In the extension phase of these studies, which lasted up to 52 weeks, mean fasting blood glucose increased by 12 mg/dL in the duloxetine delayed-release capsules group and decreased by 11.5 mg/dL in the routine care group. HbA1c increased by 0.5% in the duloxetine delayed-release group and by 0.2% in the routine care group.

5.15 Urinary Hesitation and Retention

DRIZALMA SPRINKLE is in a class of drugs known to affect urethral resistance. If symptoms of urinary hesitation develop during treatment with DRIZALMA SPRINKLE, consideration should be given to the possibility that they might be drug-related.

In post marketing experience, cases of urinary retention have been observed. In some instances of urinary retention associated with duloxetine delayed-release capsules use, hospitalization and/or catheterization has been needed.

5.16 Sexual Dysfunction

Use of SNRIs, including DRIZALMA SPRINKLE, may cause symptoms of sexual dysfunction [see Adverse Reactions (6.1)]. In male patients, SNRI use may result in ejaculatory delay or failure, decreased libido, and erectile dysfunction. In female patients, SNRI use may result in decreased libido and delayed or absent orgasm.

It is important for prescribers to inquire about sexual function prior to initiation of DRIZALMA SPRINKLE and to inquire specifically about changes in sexual function during treatment, because sexual function may not be spontaneously reported. When evaluating changes in sexual function, obtaining a detailed history (including timing of symptom onset) is important because sexual symptoms may have other causes, including the underlying psychiatric disorder. Discuss potential management strategies to support patients in making informed decisions about treatment.

6 ADVERSE REACTIONS

The following adverse reactions are discussed in more detail in other sections of the labeling:

- Suicidal Thoughts and Behaviors in Adolescents and Young Adults [see Boxed Warning and Warnings and Precautions (5.1)]
- Hepatotoxicity [see Warnings and Precautions (5.2)]
- Orthostatic Hypotension, Falls and Syncope [see Warnings and Precautions (5.3)]
- Serotonin Syndrome [see Warnings and Precautions (5.4)]
- Increased Risk of Bleeding [see Warnings and Precautions (5.5)]
- Severe Skin Reactions [see Warnings and Precautions (5.6)]
- Discontinuation Syndrome [see Warnings and Precautions (5.7)]
- Activation of Mania/Hypomania [see Warnings and Precautions (5.8)]
- Angle-Closure Glaucoma [see Warnings and Precautions (5.9)]
- Seizures [see Warnings and Precautions (5.10)]
- Increases in Blood Pressure [see Warnings and Precautions (5.11)]
- Clinically Important Drug Interactions [see Warnings and Precautions (5.12)]
- Hyponatremia [see Warnings and Precautions (5.13)]
- Urinary Hesitation and Retention [see Warnings and Precautions (5.15)]
- Sexual Dysfunction [see Warnings and Precautions (5.16)]

6.1 Clinical Trials Experience

Because clinical trials are conducted under widely varying conditions, adverse reaction rates observed in the clinical trials of a drug cannot be directly compared to rates in the clinical trials of another drug and may not reflect the rates observed in practice.

The stated frequencies of adverse reactions represent the proportion of patients who experienced, at least once, a treatment-emergent adverse reaction of the type listed.

Adverse Reactions in Adults

The data described below reflect exposure to duloxetine delayed-release capsules in placebo-controlled trials for MDD (N = 3779), GAD (N = 1018), OA (N = 503), CLBP (N = 600), and DPNP (N = 906), and FM (N = 1294). The population studied was 17 to 89 years of age; 65.7%, 60.8%, 60.6%, 42.9%, and 94.4% female; and 81.8%, 72.6%, 85.3%, 74.0%, and 85.7% Caucasian for MDD, GAD, OA and CLBP, DPNP, and FM, respectively. Most patients received doses of a total of 60 to 120 mg per day [see Clinical Studies (14)]. The data below do not include results of the trial examining the efficacy of duloxetine delayed-release in patients ≥ 65 years old for the treatment of generalized anxiety disorder; however, the adverse reactions observed in this geriatric sample were generally similar to adverse reactions in the overall adult population.

Adverse Reactions Reported as Reasons for Discontinuation of Treatment in Adult Placebo-Controlled Trials

Major Depressive Disorder:

Approximately 8.4% (319/3779) of the duloxetine delayed-release capsules-treated patients in placebo-controlled adult trials for MDD discontinued treatment due to an adverse reaction, compared with 4.6% (117/2536) of placebo-treated patients. Nausea (duloxetine delayed-release capsules 1.1%, placebo 0.4%) was the only adverse reaction reported as a reason for discontinuation and considered to be drug-related (i.e., discontinuation occurring in at least 1% of the duloxetine delayed-release capsules-treated patients and at a rate of at least twice that of placebo).

Generalized Anxiety Disorder:

Approximately 13.7% (139/1018) of the duloxetine delayed-release capsules-treated patients in placebo-controlled adult trials for GAD discontinued treatment due to an adverse reaction, compared with 5.0% (38/767) of placebo-treated patients. Common adverse reactions reported as a reason for discontinuation and considered to be drug-related (as defined above) included nausea (duloxetine delayed-release capsules 3.3%, placebo 0.4%), and dizziness (duloxetine delayed-release capsules 1.3%, placebo 0.4%).

Diabetic Peripheral Neuropathic Pain:

Approximately 12.9% (117/906) of the duloxetine delayed-release capsules-treated patients in placebo-controlled adult trials for DPNP discontinued treatment due to an adverse reaction, compared with 5.1% (23/448) for placebo-treated patients. Common adverse reactions reported as a reason for discontinuation and considered to be drug-related (as defined above) included nausea (duloxetine delayed-release capsules 3.5%, placebo 0.7%), dizziness (duloxetine delayed-release capsules 1.2%, placebo 0.4%), and somnolence (duloxetine delayed-release capsules 1.1%, placebo 0.0%).

Fibromyalgia:

Approximately 17.5% (227/1294) of the duloxetine delayed-release capsules-treated patients in 3-to 6-month placebo-controlled adult trials for FM discontinued treatment due to an adverse reaction, compared with 10.1% (96/955) for placebo-treated patients. Adverse reactions reported as a reason for discontinuation and considered to be drug-related (as defined above) included nausea (duloxetine delayed-release capsules 2.0%, placebo 0.5%), headache (duloxetine delayed-release capsules 1.2%, placebo 0.3%), somnolence (duloxetine delayed-release capsules 1.1%, placebo 0%), and fatigue (duloxetine delayed-release capsules 1.1%, placebo 0.1%).

Chronic Pain due to Osteoarthritis:

Approximately 15.7% (79/503) of the duloxetine delayed-release capsules-treated patients in 13 week, placebo-controlled adult trials for chronic pain due to OA discontinued treatment due to an adverse reaction, compared with 7.3% (37/508) for placebo-treated patients. Adverse reactions reported as a reason for discontinuation and considered to be drug-related (as defined above) included nausea (duloxetine delayed-release capsules 2.2%, placebo 1.0%).

Chronic Low Back Pain:

Approximately 16.5% (99/600) of the duloxetine delayed-release capsules-treated patients in 13 week, placebo-controlled adult trials for CLBP discontinued treatment due to an adverse reaction, compared with 6.3% (28/441) for placebo-treated patients. Adverse reactions reported as a reason for discontinuation and considered to be drug-related (as defined above) included nausea (duloxetine delayed-release capsules 3.0%, placebo 0.7%), and somnolence (duloxetine delayed-release capsules 1.0%, placebo 0.0%).

Most Common Adverse Reactions (Adults)

Diabetic Peripheral Neuropathic Pain: nausea, somnolence, decreased appetite, constipation, hyperhidrosis, and dry mouth.

Fibromyalgia: nausea, dry mouth, constipation, somnolence, decreased appetite, hyperhidrosis, and agitation.

Chronic Pain due to Osteoarthritis: nausea, fatigue, constipation, dry mouth, insomnia, somnolence, and dizziness.

Chronic Low Back Pain: nausea, dry mouth, insomnia, somnolence, constipation, dizziness, and fatigue.

Adverse Reactions Occurring at an Incidence of 5% or More Among Duloxetine Delayed-Release Capsules Treated Patients in Adult Placebo-Controlled Trials

The most commonly observed adverse reactions in duloxetine delayed-release capsule-treated patients (incidence of at least 5% and at least twice the incidence in placebo patients) were nausea, dry mouth, somnolence, constipation, decreased appetite, and hyperhidrosis. Table 2 displays the incidence of adverse reactions in placebo-controlled trials for approved indications that occurred in 5% or more of patients treated with duloxetine delayed-release capsules and with an incidence greater than placebo-treated patients.

Table 2: Adverse Reactions: Incidence of 5% or More and Greater than Placebo in Placebo-Controlled Trials of Approved Adult Populationsa

Adverse Reaction | Percentage of Patients Reporting Reaction
Adverse Reaction | Duloxetine delayed-release capsules; (N = 8100) | Placebo; (N = 5655)
Nauseac | 23 | 8
Headache | 14 | 12
Dry mouth | 13 | 5
Somnolencee | 10 | 3
Fatigueb,c | 9 | 5
Insomniad | 9 | 5
Constipationc | 9 | 4
Dizzinessc | 9 | 5
Diarrhea | 9 | 6
Decreased appetitec | 7 | 2
Hyperhidrosisc | 6 | 1
Abdominal painf | 5 | 4

a Includes adults with MDD, GAD, DPNP, FM, and chronic musculoskeletal pain. The inclusion of an event in the table is determined based on the percentages before rounding; however, the percentages displayed in the table are rounded to the nearest integer.

b Also includes asthenia.

c Events for which there was a significant dose-dependent relationship in fixed-dose studies, excluding three MDD studies which did not have a placebo lead-in period or dose titration.

d Also includes initial insomnia, middle insomnia, and early morning awakening.

e Also includes hypersomnia and sedation.

f Also includes abdominal discomfort, abdominal pain lower, abdominal pain upper, abdominal tenderness, and gastrointestinal pain.

Adverse Reactions in Pooled MDD and GAD Trials in Adults

Table 3 displays the incidence of adverse reactions in MDD and GAD placebo-controlled trials for approved indications that occurred in 2% or more of patients treated with duloxetine delayed-release capsules and with an incidence greater than placebo-treated patients.

Table 3: Adverse Reactions: Incidence of 2% or More and Greater than Placebo in MDD and GAD Placebo-Controlled Trials in Adultsa,b

System Organ Class / Adverse Reaction | Percentage of Patients Reporting Reaction
System Organ Class / Adverse Reaction | Duloxetine delayed-release capsules; (N = 4797) | Placebo; (N = 3303)
Cardiac Disorders; Palpitations | 2 | 1
Eye Disorders; Vision blurred | 3 | 1
Gastrointestinal Disorders
Nauseac | 23 | 8
Dry mouth | 14 | 6
Constipationc | 9 | 4
Diarrhea | 9 | 6
Abdominal paind | 5 | 4
Vomiting | 4 | 2
General Disorders and Administration Site; Conditions; Fatiguee | 9 | 5
Metabolism and Nutrition Disorders; Decreased appetitec | 6 | 2
Nervous System Disorders
Headache | 14 | 14
Dizzinessc | 9 | 5
Somnolencef | 9 | 3
Tremor | 3 | 1
Psychiatric Disorders
Insomniag | 9 | 5
Agitationh | 4 | 2
Anxiety | 3 | 2
Reproductive System and Breast Disorders
Erectile dysfunction | 4 | 1
Ejaculation delayedc | 2 | 1
Libido decreasedi | 3 | 1
Orgasm abnormalj | 2 | <1
Respiratory, Thoracic, and Mediastinal Disorders; Yawning | 2 | <1
Skin and Subcutaneous Tissue Disorders; Hyperhidrosis | 6 | 2

a The inclusion of an event in the table is determined based on the percentages before rounding; however, the percentages displayed in the table are rounded to the nearest integer.

b For GAD, there were no adverse reactions that were significantly different between treatments in adults ≥65 years that were also not significant in the adults <65 years.

c Events for which there was a significant dose-dependent relationship in fixed-dose studies, excluding three MDD studies which did not have a placebo lead-in period or dose titration.

d Includes abdominal pain upper, abdominal pain lower, abdominal tenderness, abdominal discomfort, and gastrointestinal pain

e Includes asthenia

f Includes hypersomnia and sedation

g Includes initial insomnia, middle insomnia, and early morning awakening

h Includes feeling jittery, nervousness, restlessness, tension and psychomotor hyperactivity

i Includes loss of libido

j Includes anorgasmia

Adverse Reactions in the DPNP, FM, OA, and CLBP Adult Trials:

Table 4 displays the incidence of adverse reactions that occurred in 2% or more of duloxetine delayed-release capsules-treated patients (determined prior to rounding) in the premarketing acute phase of DPNP, FM, OA, and CLBP placebo-controlled adult trials and with an incidence greater than placebo-treated patients.

Table 4: Adverse Reactions: Incidence of 2% or More and Greater than Placebo in DPNP, FM, OA, and CLBP Placebo-Controlled Trials in Adultsa

System Organ Class / Adverse Reaction | Percentage of Patients Reporting Reaction
System Organ Class / Adverse Reaction | Duloxetine delayed-release capsules; (N = 3303) | Placebo; (N = 2352)
Gastrointestinal Disorders; Nausea; Dry Mouthb; Constipationb; Diarrhea; Abdominal Painc; Vomiting; Dyspepsia | 23; 11; 10; 9; 5; 3; 2 | 7; 3; 3; 5; 4; 2; 1
General Disorders and Administration Site Conditions; Fatigued | 11 | 5
Infections and Infestations; Nasopharyngitis; Upper Respiratory Tract Infection; Influenza | 4; 3; 2 | 4; 3; 2
Metabolism and Nutrition Disorders; Decreased Appetiteb | 8 | 1
Musculoskeletal and Connective Tissue; Musculoskeletal Paine; Muscle Spasms | 3; 2 | 3; 2
Nervous System Disorders; Headache Somnolenceb,f Dizziness Paraesthesiag Tremorb | 13; 11; 9; 2; 2 | 8; 3; 5; 2; <1
Psychiatric Disorders; Insomniab,h; Agitationi | 10; 3 | 5; 1
Reproductive System and Breast Disorders; Erectile Dysfunctionb; Ejaculation Disorderj | 4; 2 | <1; <1
Respiratory, Thoracic, and Mediastinal Disorders; Cough | 2 | 2
Skin and Subcutaneous Tissue Disorders; Hyperhidrosis | 6 | 1
Vascular Disorders; Flushingk; Blood pressure increasedl | 3; 2 | 1; 1

a The inclusion of an event in the table is determined based on the percentages before rounding; however, the percentages displayed in the table are rounded to the nearest integer.

b Incidence of 120 mg/day is significantly greater than the incidence for 60 mg/day.

c Includes abdominal discomfort, abdominal pain lower, abdominal pain upper, abdominal tenderness and gastrointestinal pain

d Includes asthenia

e Includes myalgia and neck pain

f Includes hypersomnia and sedation

g Includes hypoaesthesia, hypoaesthesia facial, genital hypoaesthesia and paraesthesia oral

h Includes initial insomnia, middle insomnia, and early morning awakening.

i Includes feeling jittery, nervousness, restlessness, tension and psychomotor hyperactivity

j Includes ejaculation failure

k Includes hot flush

l Includes blood pressure diastolic increased, blood pressure systolic increased, diastolic hypertension, essential hypertension, hypertension, hypertensive crisis, labile hypertension, orthostatic hypertension, secondary hypertension, and systolic hypertension

Effects on Male and Female Sexual Function in Adults with MDD

Changes in sexual desire, sexual performance and sexual satisfaction often occur as manifestations of psychiatric disorders or diabetes, but they may also be a consequence of pharmacologic treatment. Because adverse sexual reactions are presumed to be voluntarily underreported, the Arizona Sexual Experience Scale (ASEX), a validated measure designed to identify sexual side effects, was used prospectively in 4 MDD placebo-controlled adult trials [see Clinical Studies (14.1)]. The ASEX scale includes five questions that pertain to the following aspects of sexual function: 1) sex drive, 2) ease of arousal, 3) ability to achieve erection (men) or lubrication (women), 4) ease of reaching orgasm, and 5) orgasm satisfaction. Positive numbers signify a worsening of sexual function from baseline. Negative numbers signify an improvement from baseline level of sexual dysfunction from baseline, which is commonly seen in depressed patients.

In these trials, male patients treated with duloxetine delayed-release capsules experienced significantly more sexual dysfunction, as measured by the total score on the ASEX and the ability to reach orgasm, than did placebo-treated male patients (see Table 5). Female patients treated with duloxetine delayed-release capsules did not experience more sexual dysfunction than on placebo-treated female patients as measured by ASEX total score. Healthcare providers should routinely inquire about possible sexual adverse reactions in patients treated with duloxetine delayed-release capsules.

Table 5: Mean Change in ASEX Scores by Gender in MDD Placebo-Controlled Adult Trials

 | Male Patientsa |  | Female Patientsa
 | Duloxetine delayed-release capsules; (n = 175) | Placebo; (n = 83) | Duloxetine delayed-release capsules; (n = 241) | Placebo; (n = 126)
ASEX Total (Items 1-5); Item 1 - Sex drive; Item 2 - Arousal; Item 3 - Ability to achieve erection (men); Lubrication (women); Item 4 - Ease of reaching orgasm; Item 5 - Orgasm satisfaction | 0.56b; -0.07; 0.01; 0.03; 0.40c; 0.09 | -1.07; -0.12; -0.26; -0.25; -0.24; -0.13 | -1.15; -0.32; -0.21; -0.17; -0.09; -0.11 | -1.07; -0.24; -0.18; -0.18; -0.13; -0.17

a n = Number of patients with non-missing change score for ASEX total

b p = 0.013 versus placebo

c p<0.001 versus placebo

Vital Sign Changes in Adults

In placebo-controlled clinical trials across approved adult populations for change from baseline to endpoint, duloxetine delayed-release capsules-treated patients had mean increases of 0.23 mm Hg in systolic blood pressure (SBP) and 0.73 mm Hg in diastolic blood pressure (DBP) compared to mean decreases of 1.09 mm Hg SBP and 0.55 mm Hg in DBP placebo-treated patients. There was no significant difference in the frequency of sustained (3 consecutive visits) elevated blood pressure [see Warnings and Precautions (5.3, 5.11)].

Duloxetine delayed-release capsules treatment, for up to 26 weeks in placebo-controlled trials across approved adult populations, typically caused a small increase in heart rate for change from baseline to endpoint compared to placebo of up to 1.37 beats per minute (increase of 1.20 beats per minute in duloxetine delayed-release capsules-treated patients, decrease of 0.17 beats per minute in placebo-treated patients).

Laboratory Changes in Adults

Duloxetine delayed-release capsules treatment in placebo-controlled clinical trials across approved adult populations, was associated with small mean increases from baseline to endpoint in ALT, AST, CPK, and alkaline phosphatase; infrequent, modest, transient, abnormal values were observed for these analytes in duloxetine delayed-release capsules-treated patients when compared with placebo-treated patients [see Warnings and Precautions (5.2)]. High bicarbonate, cholesterol, and abnormal (high or low) potassium, were observed more frequently in duloxetine delayed-release capsules treated patients compared to placebo-treated patients.

Other Adverse Reactions Observed During the Premarketing and Postmarketing Clinical Trial Evaluation of Duloxetine Delayed-Release Capsules in Adults

Following is a list of adverse reactions reported by patients treated with duloxetine delayed-release capsules in clinical trials. In clinical trials of all approved adult populations, 34,756 patients were treated with duloxetine delayed-release capsules. Of these, 26.9% (9337) took duloxetine delayed-release capsules for at least 6 months, and 12% (4317) for at least one year. The following listing is not intended to include reactions (1) already listed in previous tables or elsewhere in labeling, (2) for which a drug cause was remote, (3) which were so general as to be uninformative, (4) which were not considered to have significant clinical implications, or (5) which occurred at a rate equal to or less than placebo.

Reactions are categorized by body system according to the following definitions: frequent adverse reactions are those occurring in at least 1/100 patients; infrequent adverse reactions are those occurring in 1/100 to 1/1000 patients; rare reactions are those occurring in fewer than 1/1000 patients.

Cardiac Disorders- Frequent: palpitations; Infrequent: myocardial infarction, tachycardia, and Takotsubo cardiomyopathy.

Ear and Labyrinth Disorders- Frequent: vertigo; Infrequent: ear pain and tinnitus.

Endocrine Disorders- Infrequent:hypothyroidism.

Eye Disorders- Frequent: vision blurred; Infrequent: diplopia, dry eye, and visual impairment.

Gastrointestinal Disorders- Frequent: flatulence; Infrequent: dysphagia, eructation, gastritis, gastrointestinal hemorrhage, halitosis, and stomatitis; Rare: gastric ulcer.

General Disorders and Administration Site Conditions- Frequent: chills/rigors; Infrequent: falls, feeling abnormal, feeling hot and/or cold, malaise, and thirst; Rare: gait disturbance.

Infections and Infestations- Infrequent: gastroenteritis and laryngitis.

Investigations - Frequent: weight increased, weight decreased; Infrequent: blood cholesterol increased.

Metabolism and Nutrition Disorders- Infrequent: dehydration and hyperlipidemia; Rare: dyslipidemia.

Musculoskeletal and Connective Tissue Disorders- Frequent: musculoskeletal pain; Infrequent: muscle tightness and muscle twitching.

Nervous System Disorders- Frequent: dysgeusia, lethargy, and paraesthesia/hypoesthesia; Infrequent:

disturbance in attention, dyskinesia, myoclonus, and poor quality sleep; Rare: dysarthria.

Psychiatric Disorders- Frequent: abnormal dreams and sleep disorder; Infrequent: apathy, bruxism, disorientation/confusional state, irritability, mood swings, and suicide attempt; Rare: completed suicide.

Renal and Urinary Disorders- Frequent: urinary frequency; Infrequent: dysuria, micturition urgency, nocturia, polyuria, and urine odor abnormal.

Reproductive System and Breast Disorders- Frequent: anorgasmia/orgasm abnormal; Infrequent:

menopausal symptoms, sexual dysfunction, and testicular pain; Rare: menstrual disorder.

Respiratory, Thoracic and Mediastinal Disorders- Frequent: yawning, oropharyngeal pain; Infrequent: throat tightness.

Skin and Subcutaneous Tissue Disorders- Frequent: pruritus; Infrequent: cold sweat, dermatitis contact, erythema, increased tendency to bruise, night sweats, and photosensitivity reaction; Rare: ecchymosis.

Vascular Disorders- Frequent: hot flush; Infrequent: flushing, orthostatic hypotension, and peripheral coldness.

Adverse Reactions Observed in Placebo-Controlled Clinical Trials in Pediatric Patients

The data described below reflect exposure to duloxetine delayed-release capsules in pediatric, 10 week, placebo-controlled trials for MDD (N = 341) and GAD (N = 135). The population studied (N = 476) was 7 to 17 years of age with 42.4% children age 7 to 11 years of age, 50.6% female, and 68.6% white. Patients received 30 to 120 mg per day during placebo-controlled acute treatment studies. Additional data come from the overall total of 822 pediatric patients (age 7 to 17 years of age) with 41.7% children age 7 to 11 years of age and 51.8% female exposed to duloxetine delayed-release capsules in MDD and GAD clinical trials up to 36 weeks in length, in which most patients received 30 to 120 mg per day. The safety and effectiveness of DRIZALMA SPRINKLE have not been established in pediatric patients with major depressive disorder (MDD), diabetic peripheral neuropathic pain, or chronic musculoskeletal pain.

Pediatric Clinical Trial Database

The adverse drug reaction profile observed in pediatric clinical trials in pediatric patients aged 7 to 17 years old was consistent with the adverse drug reaction profile observed in adult clinical trials. The specific adverse drug reactions observed in adult patients can be expected to be observed in pediatric patients [see Adverse Reactions (6.1)]. The most common (≥5% and twice placebo) adverse reactions observed in pediatric clinical trials include: nausea, diarrhea, decreased weight, and dizziness.

Adverse Reactions in Pediatric Patients Aged 7 to 17 Years Old with MDD and GAD

Table 6 provides the incidence of adverse reactions in MDD and GAD pediatric placebo- controlled trials that occurred in greater than 2% of patients treated with duloxetine delayed-release capsules and with an incidence greater than placebo. DRIZALMA SPRINKLE is not approved for the treatment of MDD in pediatric patients [see Use in Specific Populations (8.4)]

Table 6: Adverse Reactions: Incidence of 2% or More and Greater than Placebo in three 10 week Pediatric Placebo-Controlled Trialsin MDDa and GADb

System Organ Class/Adverse Reaction | Percentage of Pediatric Patients Reporting Reaction
System Organ Class/Adverse Reaction | Duloxetine delayed-release capsules; (N = 476) | Placebo (N = 362)
Gastrointestinal Disorders; Nausea; Abdominal Painc; Vomiting; Diarrhea; Dry Mouth | 18; 13; 9; 6; 2 | 8; 10; 4; 3; 1
General Disorders and Administration Site; Conditions; Fatigued | 7 | 5
Investigations; Decreased Weighte | 14 | 6
Metabolism and Nutrition Disorders; Decreased Appetite | 10 | 5
Nervous System Disorders; Headache; Somnolencef; Dizziness | 18; 11; 8 | 13; 6; 4
Psychiatric Disorders; Insomniag | 7 | 4
Respiratory, Thoracic, and Mediastinal; Disorders; Oropharyngeal Pain; Cough | 4; 3 | 2; 1

a DRIZALMA SPRINKLE is not approved for the treatment of pediatric MDD [see Use in Specific Populations (8.4)].

bThe inclusion of an event in the table is determined based on the percentages before rounding; however, the percentages displayed in the table are rounded to the nearest integer.

c Also includes abdominal pain upper, abdominal pain lower, abdominal tenderness, abdominal discomfort, and gastrointestinal pain.

d Also includes asthenia.

e Frequency based on weight measurement meeting potentially clinically significant threshold of ≥3.5% weight loss

(N = 467 duloxetine delayed-release capsules; N = 354 Placebo).

f Also includes hypersomnia and sedation.

g Also includes initial insomnia, insomnia, middle insomnia, and terminal insomnia.

Other adverse reactions that occurred at an incidence of less than 2% and were reported by more duloxetine delayed-release capsules treated patients than placebo treated patients in pediatric MDD and GAD clinical trials included abnormal dreams (including nightmare), anxiety, flushing (including hot flush), hyperhidrosis, palpitations, pulse increased, and tremor (DRIZALMA SPRINKLE is not approved for the treatment of pediatric MDD).

The most commonly reported symptoms following discontinuation of duloxetine delayed-release capsules in pediatric clinical trials have included headache, dizziness, insomnia, and abdominal pain [see Warnings and Precautions (5.7)].

Growth (Height and Weight) in Pediatric Patients 7 to 17 Years Old with GAD and MDD

Decreased appetite and weight loss have been observed in association with the use of SSRIs and SNRIs. Pediatric patients treated with duloxetine delayed-release capsules in clinical trials experienced a 0.1kg mean decrease in weight at 10 weeks, compared with a mean weight gain of approximately 0.9 kg in placebo-treated patients. The proportion of patients who experienced a clinically significant decrease in weight (≥3.5%) was greater in the duloxetine delayed-release capsules group than in the placebo group (16% and 6%, respectively). Subsequently, over the 4- to 6-month uncontrolled extension periods, duloxetine delayed-release capsules-treated patients on average trended toward recovery to their expected baseline weight percentile based on population data from age- and sex-matched peers.

In studies up to 9 months, duloxetine delayed-release capsules-treated pediatric patients experienced an increase in height of 1.7 cm on average (2.2 cm increase in patients [7 to 11 years of age] and 1.3 cm increase in patients [12 to 17 years of age]). While height increase was observed during these studies, a mean decrease of 1% in height percentile was observed (decrease of 2% in patients [7 to 11 years of age] and increase of 0.3% in patients [12 to 17 years of age]). Weight and height should be monitored regularly in pediatric patients treated with DRIZALMA SPRINKLE.

Additional pediatric use information is approved for Eli Lilly and Company, Inc.’s CYMBALTA (duloxetine delayed-release capsules). However, due to Eli Lilly and Company Inc.’s marketing exclusivity rights, this drug product is not labeled with that pediatric information.

6.2 Postmarketing Experience

The following adverse reactions have been identified during post approval use of duloxetine delayed-release capsules. Because these reactions are reported voluntarily from a population of uncertain size, it is not always possible to reliably estimate their frequency or establish a causal relationship to drug exposure.

Adverse reactions reported since market introduction that were temporally related to duloxetine delayed-release capsules therapy and not mentioned elsewhere in labeling include: acute pancreatitis, anaphylactic reaction, aggression and anger (particularly early in treatment or after treatment discontinuation), angioneurotic edema, angle-closure glaucoma, colitis (microscopic or unspecified), cutaneous vasculitis (sometimes associated with systemic involvement), extrapyramidal disorder, galactorrhea, gynecological bleeding, hallucinations, hyperglycemia, hyperprolactinemia, hypersensitivity, hypertensive crisis, muscle spasm, rash, restless legs syndrome, seizures upon treatment discontinuation, supraventricular arrhythmia, tinnitus (upon treatment discontinuation), trismus, and urticaria.

7 DRUG INTERACTIONS

7.1 Drugs Having Clinically Important Interactions with DRIZALMA SPRINKLE

Table 7: Clinically Important Drug Interactions

Monoamine Oxidase Inhibitors (MAOIs)
Clinical Impact | Concomitant use of SSRIs and SNRIs including duloxetine with MAOIs increases the risk of serotonin syndrome.
Intervention | •The use of MAOIs intended to treat psychiatric disorders with duloxetine or within 5 days of stopping treatment with duloxetine is contraindicated [see Contraindications (4) and Warnings and Precautions (5.4)].•The use of duloxetine delayed-release capsules within 14 days of stopping an MAOI intended to treat psychiatric disorders is also contraindicated [see Contraindications (4) and Warnings and Precautions (5.4)].•Starting duloxetine in a patient who is being treated with MAOIs is also contraindicated [see Dosage and Administration (2.10), Contraindications (4), Warnings and Precautions (5.4)].
Examples | Selegiline, tranylcypromine, isocarboxazid, phenelzine, linezolid, intravenous methylene blue
Other Serotonergic Drugs
Clinical Impact | Concomitant use of duloxetine with other serotonergic drugs increases the risk of serotonin syndrome.
Intervention | •Patients should be made aware of a potential increased risk for serotonin syndrome, particularly during treatment initiation and dose increases.•Monitor for symptoms of serotonin syndrome when duloxetine is used concomitantly with other drugs that may affect the serotonergic neurotransmitter systems.•Treatment with duloxetine delayed-release capsules and any concomitant serotonergic agents, should be discontinued immediately if the above events occur and supportive symptomatic treatment should be initiated [see Warnings and Precautions (5.4)].
Examples | Other SNRIs, SSRIs, triptans, tricyclic antidepressants, opioids, lithium, tryptophan, buspirone, amphetamines, and St. John’s Wort
Inhibitors of CYP1A2
Clinical Impact | Concomitant use of duloxetine with CYP1A2 inhibitors increases AUC, Cmax, t1/2 of duloxetine.
Intervention | Avoid concomitant use of duloxetine delayed-release capsules with potent CYP1A2 inhibitors [see Warnings and Precautions (5.12), Clinical Pharmacology (12.3)].
Examples | Fluvoxamine, cimetidine, ciprofloxacin, enoxacin
Dual Inhibition of CYP1A2 and CYP2D6
Clinical Impact | Concomitant administration of duloxetine with potent CYP1A2 inhibitors to CYP2D6 poor metabolizers results in increased AUC and Cmax of duloxetine.
Intervention | Avoid co-administration of duloxetine delayed-release capsules and potent CYP1A2 inhibitors to CYP2D6 poor metabolizers [see Clinical Pharmacology (12.3)].
Examples | Fluvoxamine, cimetidine, ciprofloxacin, enoxacin
Drugs that Interfere with Hemostasis
Clinical Impact | Concomitant use of duloxetine with an antiplatelet or anticoagulant drug may potentiate the risk of bleeding.
Intervention | Closely monitor for bleeding for patients receiving an antiplatelet or anticoagulant drug when duloxetine is initiated or discontinued [Warnings and Precaution (5.5)].
Examples | NSAIDs, aspirin, warfarin
Inhibitors of CYP2D6
Clinical Impact | Concomitant use of duloxetine with CYP2D6 inhibitors increase AUC of duloxetine. Greater degrees of inhibition are expected with higher doses of CYP2D6 inhibitors.
Intervention | Exercise caution when co-administering duloxetine delayed-release capsules and potent CYP2D6 inhibitors [see Warnings and Precautions (5.12), Clinical Pharmacology (12.3)].
Examples | Paroxetine, fluoxetine, quinidine
Drugs Metabolized by CYP2D6
Clinical Impact | Concomitant use of duloxetine increases AUC of a drug primarily metabolized by CYP2D6 which may increase the risk of toxicity of the CYP2D6 substrate drug.
Intervention | Monitor plasma concentrations of CYP2D6 substrate and reduce dosage of CYP2D6 substrate drug if necessary [see Warnings and Precautions (5.12), Clinical Pharmacology (12.3)].
Examples | TCAs (nortriptyline, amitriptyline, imipramine, desipramine); phenothiazines (thioridazine); Type 1C antiarrhythmics (propafenone, flecainide)
Drugs that Affect Gastric Acidity
Clinical Impact | In patients with conditions that may slow gastric emptying (e.g., some diabetics) and drugs that raise the gastrointestinal pH may lead to earlier the release of duloxetine.
Intervention | Use with caution [see Clinical Pharmacology (12.3)].
Examples | Aluminum-and magnesium-containing antacids, famotidine, proton pump inhibitors
Drugs Metabolized by CYP1A2
Clinical Impact | Concomitant use of duloxetine with CYP1A2 substrates may increase the AUC of CYP1A2 substrate.
Intervention | Use with caution [see Clinical Pharmacology (12.3)].
Examples | Theophylline, caffeine
CNS Drugs
Clinical Impact | Concomitant use of duloxetine with other centrally acting drugs may increase the CNS effects of duloxetine.
Intervention | Use with caution [see Warnings and Precautions (5.12)].
Examples | Centrally acting CNS drugs
Drugs Highly Bound to Plasma Protein
Clinical Impact | Concomitant use of duloxetine with highly protein bound drugs may cause increased free concentrations of the other drug, potentially resulting in adverse reactions.
Intervention | Use with caution [see Clinical Pharmacology (12.3)].
Examples | Highly plasma protein binding drugs
Alcohol
Clinical Impact | Concomitant use of duloxetine and alcohol may cause liver injury or aggravate pre-existing liver disease.
Intervention | Avoid use patients with chronic liver disease or heavy alcohol use [see Dosage and Administration (2.7), Warnings and Precautions (5.2, 5.12)].

8 USE IN SPECIFIC POPULATIONS

8.1 Pregnancy

Pregnancy Exposure Registry

There is a pregnancy exposure registry that monitors pregnancy outcomes in women exposed to antidepressants during pregnancy. Healthcare providers are encouraged to register patients by calling the National Pregnancy Registry for Antidepressants at 1-844-405-6185 or visiting online at https://womensmentalhealth.org/clinical-and-research-programs/pregnancyregistry/antidepressants/

Risk Summary

Based on data from published observational studies, exposure to SNRIs, particularly in the month before delivery, has been associated with a less than 2-fold increase in the risk of postpartum hemorrhage [see Warnings and Precautions (5.5) and Clinical Considerations].

Data from a postmarketing retrospective cohort study indicate that use of duloxetine in the month before delivery may be associated with an increased risk of postpartum hemorrhage. Data from published literature and from a postmarketing retrospective cohort study have not identified a clear drug-associated risk of major birth defects or other adverse developmental outcomes (see Data). There are risks associated with untreated depression in pregnancy and with exposure to SNRIs and SSRIs, including DRIZALMA SPRINKLE, during pregnancy (see Clinical Considerations).

In rats and rabbits treated with duloxetine during the period of organogenesis, fetal weights were decreased but there was no evidence of developmental effects at doses up to 3 and 6 times, respectively, the maximum recommended human dose (MRHD) of 120 mg/day given to adolescents on a mg/m^2 basis. When duloxetine was administered orally to pregnant rats throughout gestation and lactation, pup weights at birth and pup survival to 1 day postpartum were decreased at a dose 2 times the MRHD given to adolescents on a mg/m^2 basis. At this dose, pup behaviors consistent with increased reactivity, such as increased startle response to noise and decreased habituation of locomotor activity were observed. Post-weaning growth was not adversely affected.

The estimated of background risk of major birth defects and miscarriage for the indicated population is unknown. All pregnancies have a background risk of birth defect, loss, or other adverse outcomes. In the U.S. general population, the estimated background risk of major birth defects and miscarriage in clinically recognized pregnancies is 2% to 4% and 15% to 20%, respectively.

Clinical Considerations

Disease-associated Maternal and/or Embryo/Fetal Risk

Women who discontinued antidepressants during pregnancy are more likely to experience a relapse of major depression than women who continued antidepressants. This finding is from a prospective, longitudinal study that followed 201 pregnant women with a history of major depressive disorder who were euthymic and taking antidepressants at the beginning of pregnancy. Consider the risk of untreated depression when discontinuing or changing treatment with antidepressant medication during pregnancy and the postpartum.

Pregnant women with fibromyalgia are at increased risk for adverse maternal and infant outcomes including preterm premature rupture of membranes, preterm birth, small for gestational age, intrauterine growth restriction, placental disruption, and venous thrombosis. It is not known if these adverse maternal and fetal outcomes are a direct result of fibromyalgia or other comorbid factors.

Maternal Adverse Reactions

Use of DRIZALMA SPRINKLE in the month before delivery may be associated with an increased risk of postpartum hemorrhage [see Warnings and Precautions (5.5)].

Fetal/Neonatal Adverse Reaction

Neonates exposed to duloxetine and other SNRIs or SSRIs late in the third trimester have developed complications requiring prolonged hospitalization, respiratory support, and tube feeding. Such complications can arise immediately upon delivery. Reported clinical findings have included respiratory distress, cyanosis, apnea, seizures, temperature instability, feeding difficulty, vomiting, hypoglycemia, hypotonia, hypertonia, hyperreflexia, tremor, jitteriness, irritability, and constant crying. These findings are consistent with either a direct toxic effect of the SNRIs or SSRIs, or possibly, a drug discontinuation syndrome. It should be noted that, in some cases, the clinical picture is consistent with serotonin syndrome [see Warnings and Precautions (5.4)].

Data

Human Data

Data from a postmarketing retrospective claims-based cohort study found an increased risk for postpartum hemorrhage among 955 pregnant women exposed to duloxetine in the last month of pregnancy compared to 4,128,460 unexposed pregnant women (adjusted relative risk: 1.53; 95% CI: 1.08-2.18). The same study did not find a clinically meaningful increase in the risk for major birth defects in the comparison of 2532 women exposed to duloxetine in the first trimester of pregnancy to 1,284,827 unexposed women after adjusting for several confounders. Methodologic limitations include possible residual confounding, misclassification of exposure and outcomes, lack of direct measures of disease severity, and lack of information about alcohol use, nutrition, and over-the-counter medication exposures.

Animal Data

In animal reproduction studies, duloxetine has been shown to have adverse effects on embryo/fetal and postnatal development.

When duloxetine was administered orally to pregnant rats and rabbits during the period of organogenesis, there was no evidence of malformations or developmental variations at doses up to 45 mg/kg/day (3 and 6 times, respectively, the MRHD of 120 mg/day given to adolescents on a mg/m^2 basis. However, fetal weights were decreased at this dose, with a no-effect dose of 10 mg/kg/day (approximately equal to the MRHD in rats and 2 times the MRHD in rabbits).

When duloxetine was administered orally to pregnant rats throughout gestation and lactation, the survival of pups to 1 day postpartum and pup body weights at birth and during the lactation period were decreased at a dose of 30 mg/kg/day (2 times the MRHD given to adolescents on a mg/m^2 basis); the no-effect dose was 10 mg/kg/day. Furthermore, behaviors consistent with increased reactivity, such as increased startle response to noise and decreased habituation of locomotor activity, were observed in pups following maternal exposure to 30 mg/kg/day. Post-weaning growth and reproductive performance of the progeny were not affected adversely by maternal duloxetine treatment.

8.2 Lactation

Risk Summary

Data from the published literature report the presence of duloxetine in human milk (see Data). There are reports of sedation, poor feeding, and poor weight gain in infants exposed to duloxetine through breast milk (see Clinical Considerations). There are no data on the effect of duloxetine on milk production. The developmental and health benefits of breastfeeding should be considered along with the mother’s clinical need for DRIZALMA SPRINKLE and any potential adverse effects on the breastfed child from DRIZALMA SPRINKLE or from the underlying maternal condition.

Clinical Considerations

Infants exposed to DRIZALMA SPRINKLE should be monitored for sedation, poor feeding and poor weight gain.

Data

Disposition of duloxetine was studied in 6 lactating women who were at least 12 weeks postpartum and had elected to wean their infants. The women were given 40 mg of duloxetine delayed-release capsules twice daily for 3.5 days. The peak concentration measured in breast milk occurred at a median of 3 hours after the dose. The amount of duloxetine in breast milk was approximately 7 mcg/day while on that dose; the estimated daily infant dose was approximately 2 mcg/kg/day, which is less than 1% of the maternal dose. The presence of duloxetine metabolites in breast milk was not examined.

8.4 Pediatric Use

The safety and effectiveness of DRIZALMA SPRINKLE have been established for treatment of generalized anxiety disorder (GAD) in pediatric patients ages 7 to 17 years of age. The safety and effectiveness of DRIZALMA SPRINKLE have not been established in pediatric patients with major depressive disorder (MDD), diabetic peripheral neuropathic pain, or chronic musculoskeletal pain.

Antidepressants increased the risk of suicidal thoughts and behavior in pediatric patients. Monitor all pediatric patients being treated with antidepressants for clinical worsening and emergence of suicidal thoughts and behaviors, especially during the initial few months of treatment, or at times of dosage changes [see Warnings and Precautions (5.1)]. Perform regular monitoring of weight and growth in pediatric patients treated with DRIZALMA SPRINKLE [see Adverse Reactions (6.1)].

Generalized Anxiety Disorder

Use of DRIZALMA SPRINKLE for the treatment of GAD in patients 7 to 17 years of age is supported by one 10-week, placebo- controlled trial (GAD-6). The study included 272 pediatric patients with GAD of which 47% were 7 to 11 years of age (53% were 12 to 17 years of age). Duloxetine delayed-release capsules demonstrated superiority over placebo as measured by greater improvement in the Pediatric Anxiety Rating Scale (PARS) for GAD severity score [see Clinical Studies (14.3)].

The safety and effectiveness of DRIZALMA SPRINKLE for the treatment of GAD in pediatric patients less than 7 years of age have not been established.

Fibromyalgia

The safety and effectiveness of DRIZALMA SPRINKLE for the treatment of fibromyalgia in patients less than 13 years of age have not been established.

Additional pediatric use information is approved for Eli Lilly and Company, Inc.’s CYMBALTA (duloxetine delayed-release capsules). However, due to Eli Lilly and Company Inc.’s marketing exclusivity rights, this drug product is not labeled with that pediatric information.

Major Depressive Disorder

The safety and effectiveness of DRIZALMA SPRINKLE have not been established in pediatric patients for the treatment of MDD. Efficacy of duloxetine delayed-release capsules was not demonstrated in two 10 week, placebo-controlled trials with 800 pediatric patients with MDD, aged 7 to 17 years old with MDD. Neither duloxetine delayed-release capsules nor an active control (approved for treatment of pediatric MDD) was superior to placebo.

The most frequently observed adverse reactions in the clinical trials included nausea, headache, decreased weight, and abdominal pain. Decreased appetite and weight loss have been observed in association with the use of SSRIs and SNRIs. Juvenile Animal Toxicology Data

Duloxetine administration to young rats from post-natal day 21 (weaning) through post-natal day 90 (adult) resulted in decreased body weights that persisted into adulthood, but recovered when drug treatment was discontinued; slightly delayed (~1.5 days) sexual maturation in females, without any effect on fertility; and a delay in learning a complex task in adulthood, which was not observed after drug treatment was discontinued. These effects were observed at the high dose of 45 mg/kg/day (2 times the MRHD, for a child); the no-effect-level was 20 mg/kg/day (≈1 times the MRHD, for a child).

8.5 Geriatric Use

Geriatric Exposure in Premarketing Clinical Trials of duloxetine delayed-release capsules

•Of the 2,418 patients in MDD trials, 6% (143) were 65 years of age or over.•Of the 1041 patients in CLBP trials, 21% (221) were 65 years of age or over.•Of the 487 patients in OA trials, 41% (197) were 65 years of age or over.•Of the 1,074 patients in the DPNP trials, 33% (357) were 65 years of age or over.•Of the 1,761 patients in FM trials, 8% (140) were 65 years of age or over.

In the MDD, GAD, DPNP, FM, OA, and CLBP studies, no overall differences in safety or effectiveness were generally observed between these patients and younger adult patients, and other reported clinical experience has not identified differences in responses between these geriatric and younger adult patients, but greater sensitivity of some older patients cannot be ruled out.

SSRIs and SNRIs, including duloxetine delayed-release capsules have been associated with clinically significant hyponatremia in geriatric patients, who may be at greater risk for this adverse reaction [see Warnings and Precautions (5.13)].

In an analysis of data from all placebo-controlled-trials, patients treated with duloxetine delayed-release capsules reported a higher rate of falls compared to patients treated with placebo. The increased risk appears to be proportional to a patient’s underlying risk for falls. Underlying risk appears to increase steadily with age. As geriatric patients tend to have a higher prevalence of risk factors for falls such as medications, medical comorbidities and gait disturbances, the impact of increasing age by itself on falls during treatment with duloxetine delayed-release capsules is unclear. Falls with serious consequences including bone fractures and hospitalizations have been reported with duloxetine delayed-release capsules use [see Warnings and Precautions (5.3) and Adverse Reactions (6.1)].

The pharmacokinetics of duloxetine after a single dose of 40 mg were compared in healthy elderly females (65 to 77 years) and healthy middle-age females (32 to 50 years). There was no difference in the Cmax, but the AUC of duloxetine was somewhat (about 25%) higher and the half-life about 4 hours longer in the elderly females. Population pharmacokinetic analyses suggest that the typical values for clearance decrease by approximately 1% for each year of age between 25 to 75 years of age; but age as a predictive factor only accounts for a small percentage of between-patient variability. Dosage adjustment based on the age of the adult patient is not necessary.

8.6 Gender

Duloxetine’s half-life is similar in men and women. Dosage adjustment based on gender is not necessary.

8.7 Smoking Status

Duloxetine bioavailability (AUC) appears to be reduced by about one-third in smokers. Dosage modifications are not recommended for smokers.

8.8 Race

No specific pharmacokinetic study was conducted to investigate the effects of race.

8.9 Hepatic Impairment

Patients with clinically evident hepatic impairment have decreased duloxetine metabolism and elimination. After a single 20 mg dose of duloxetine delayed-release capsules, 6 cirrhotic patients with moderate liver impairment (Child-Pugh Class B) had a mean plasma duloxetine clearance about 15% that of age- and gender-matched healthy subjects, with a 5 fold increase in mean exposure (AUC). Although Cmax was similar to normals in the cirrhotic patients, the half-life was about 3 times longer [see Dosage and Administration (2.8) and Warnings and Precautions (5.14)].

8.10 Severe Renal Impairment

Limited data are available on the effects of duloxetine in patients with end-stage renal disease (ESRD). After a single 60 mg dose of duloxetine, Cmax and AUC values were approximately 100% greater in patients with end-stage renal disease receiving chronic intermittent hemodialysis than in subjects with normal renal function. The elimination half-life, however, was similar in both groups. The AUCs of the major circulating metabolites, 4-hydroxy duloxetine glucuronide and 5-hydroxy, 6-methoxy duloxetine sulfate, largely excreted in urine, were approximately 7 to 9 fold higher and would be expected to increase further with multiple dosing. Population PK analyses suggest that mild to moderate degrees of renal impairment (estimated CrCl 30 to 80 mL/min) have no significant effect on duloxetine apparent clearance [see Dosage and Administration (2.8) and Warnings and Precautions (5.14)].

9 DRUG ABUSE AND DEPENDENCE

9.2 Abuse

In animal studies, duloxetine did not demonstrate barbiturate-like (depressant) abuse potential.

While duloxetine delayed-release capsules have not been systematically studied in humans for its potential for abuse, there was no indication of drug-seeking behavior in the clinical trials. However, it is not possible to predict on the basis of premarketing experience the extent to which a CNS active drug will be misused, diverted, and/or abused once marketed. Consequently, physicians should carefully evaluate patients for a history of drug abuse and follow such patients closely, observing them for signs of misuse or abuse of duloxetine delayed-release capsules (e.g., development of tolerance, incrementation of dose, drug-seeking behavior).

9.3 Dependence

In drug dependence studies, duloxetine did not demonstrate dependence-producing potential in rats.

10 OVERDOSAGE

10.1 Signs and Symptoms

In postmarketing experience, fatal outcomes have been reported for acute overdoses, primarily with mixed overdoses, but also with duloxetine only, at doses as low as 1000 mg. Signs and symptoms of overdose (duloxetine alone or with mixed drugs) included somnolence, coma, serotonin syndrome, seizures, syncope, tachycardia, hypotension, hypertension, and vomiting.

10.2 Management of Overdose

There is no specific antidote to a duloxetine overdosage, but if serotonin syndrome ensues, specific treatment (such as with cyproheptadine and/or temperature control) may be considered.

In case of acute overdose, treatment should consist of those general measures employed in the management of overdose with any drug, such as assuring an an adequate airway, oxygenation, and ventilation and monitoring cardiac rhythm and vital signs. Gastric lavage with a large-bore orogastric tube with appropriate airway protection, if needed, may be indicated if performed soon after ingestion or in symptomatic patients. Induction of emesis is not recommended.

Activated charcoal may be useful in limiting absorption of duloxetine from the gastrointestinal tract. Administration of activated charcoal has been shown to decrease AUC and Cmax by an average of one-third, although some patients had a limited effect of activated charcoal. Due to the large volume of distribution of duloxetine, forced diuresis, dialysis, hemoperfusion, and exchange transfusion are unlikely to be beneficial.

In managing overdose, the possibility of multiple drug involvement should be considered. A specific caution involves patients who overdose with duloxetine delayed-release capsules and tricyclic antidepressants. In such a case, decreased clearance of the parent tricyclic and/or its active metabolite may increase the possibility of clinically significant sequelae and extend the time needed for close medical observation [see Warnings and Precautions (5.4) and Drug Interactions (7)]. In case of an overdose, consult a Certified Poison Control Center (1-800-222-1222 or www.poison.org) for up-to-date guidance and advice.

11 DESCRIPTION

Duloxetine hydrochloride is a selective serotonin and norepinephrine reuptake inhibitor (SNRI). The chemical name of duloxetine hydrochloride is (+)-(S)-N-methyl-γ-(1-naphthyloxy)-2-thiophenepropylamine hydrochloride. The molecular formula is C18H19NOS•HCl, which corresponds to a molecular weight of 333.88. The structural formula is:

Duloxetine hydrochloride, USP is a white to off-white powder, which is freely soluble in methanol, soluble in dichloromethane, and slightly soluble in water. The molecular formula of duloxetine free base is C18H19NOS and its molecular weight is 297.38.

Each DRIZALMA SPRINKLE (duloxetine delayed-release capsule) for oral administration contains enteric-coated pellets containing a total of 22.4 mg, 33.6 mg, 44.9 mg or 67.3 mg of duloxetine hydrochloride, equivalent to 20 mg, 30 mg, 40 mg or 60 mg of duloxetine free base, respectively. These enteric-coated pellets are designed to prevent degradation of the drug in the acidic environment of the stomach. Inactive ingredients of the pellets include ascorbic acid, hypromellose, hypromellose phthalate, polyethylene glycol, starch, sucrose, sugar spheres, talc, titanium dioxide, and triethyl citrate. The capsule shell ingredients for 20 mg strength are D&C Yellow 10, FD &C Blue 1, FD &C Red 40, gelatin, sodium lauryl sulfate and titanium dioxide. The capsule shell ingredients for 30 mg strength are FD &C Blue 1, FD &C Red 40 and FD &C Red 3 (present in cap), gelatin, sodium lauryl sulfate and titanium dioxide. The capsule shell ingredients for 40 mg strength are gelatin, sodium lauryl sulfate and titanium dioxide. The capsule shell ingredients for 60 mg strength are D&C Yellow 10 (present in body), FD &C Blue 1, FD &C Red 40, FD &C Red 3 (present in cap), gelatin, sodium lauryl sulfate and titanium dioxide.

The imprinting ink for 20 mg, 30 mg, 40 mg, and 60 mg strength capsules was made of ammonia solution, black iron oxide, butyl alcohol, dehydrated alcohol, isopropyl alcohol, potassium hydroxide, propylene glycol and shellac.

DRIZALMA SPRINKLE does not comply with the USP dissolution test.

12 CLINICAL PHARMACOLOGY

12.1 Mechanism of Action

Although the exact mechanisms of the antidepressant, central pain inhibitory and anxiolytic actions of duloxetine in humans are unknown, these actions are believed to be related to its potentiation of serotonergic and noradrenergic activity in the CNS.

12.2 Pharmacodynamics

Preclinical studies have shown that duloxetine is a potent inhibitor of neuronal serotonin and norepinephrine reuptake and a less potent inhibitor of dopamine reuptake. Duloxetine has no significant affinity for dopaminergic, adrenergic, cholinergic, histaminergic, opioid, glutamate, and GABA receptors in vitro. Duloxetine does not inhibit monoamine oxidase (MAO).

Duloxetine is in a class of drugs known to affect urethral resistance [see Warnings and Precautions (5.15)].

Cardiac Electrophysiology

The effect of duloxetine delayed-release capsules 160 mg and 200 mg administered twice daily (2.7 and 3.3 times the maximum recommended dosage, respectively) to steady state was evaluated in a randomized, double-blinded, two-way crossover study in 117 healthy female adult subjects. No QT interval prolongation was detected. Duloxetine delayed-release capsules appears to be associated with concentration-dependent but not clinically meaningful QT shortening.

12.3 Pharmacokinetics

Duloxetine hydrochloride pharmacokinetics are dose proportional over the therapeutic range. Steady-state plasma concentrations are typically achieved after 3 days of dosing.

Absorption

After oral duloxetine delayed-release capsules administration, duloxetine hydrochloride is well absorbed. Peak plasma concentration of duloxetine is attained at 5 hours following administration of duloxetine delayed-release capsules. There is a 3 hour delay in absorption and a one- third increase in apparent clearance of duloxetine after an evening dose as compared to a morning dose.

Effect of food

Compared to fasted state administration, high-fat, high-calorie meal (containing approximately 150 kcal from protein, 250 kcal from carbohydrates and 500 kcal from fat) did not have a significant effect on Cmax and AUC of duloxetine hydrochloride. However, Tmax of duloxetine hydrochloride delayed by approximately 1.7 hours with the administration of high-fat, high-calorie meal.

Duloxetine delayed-release capsules administered under fasting conditions to healthy adults by sprinkling the entire contents on one-tablespoon (15 mL) of applesauce did not significantly affect Tmax, Cmax, and AUC of duloxetine.

Distribution

The apparent volume of distribution averages about 1640 L. Duloxetine is highly bound (>90%) to proteins in human plasma, binding primarily to albumin and α1-acid glycoprotein. The interaction between duloxetine and other highly protein bound drugs has not been fully evaluated. Plasma protein binding of duloxetine is not affected by renal or hepatic impairment.

Elimination

Metabolism

Biotransformation and disposition of duloxetine in humans have been determined following oral administration of ^14C-labeled duloxetine. Duloxetine comprises about 3% of the total radiolabeled material in the plasma, indicating that it undergoes extensive metabolism to numerous metabolites. The major biotransformation pathways for duloxetine involve oxidation of the naphthyl ring followed by conjugation and further oxidation. Both CYP1A2 and CYP2D6 catalyze the oxidation of the naphthyl ring in vitro. Metabolites found in plasma include 4-hydroxy duloxetine glucuronide and 5-hydroxy, 6-methoxy duloxetine sulfate. Duloxetine undergoes extensive metabolism, but the major circulating metabolites have not been shown to contribute significantly to the pharmacologic activity of duloxetine.

Excretion

Only trace (<1% of the dose) amounts of unchanged duloxetine are present in the urine. Most (about 70%) of the duloxetine dose appears in the urine as metabolites of duloxetine; about 20% is excreted in the feces. Mean terminal half-life was 12.4 hours (range 7.8 to 22.2 hour) in subjects receiving a single dose DRIZALMA SPRINKLE.

Specific Populations

Pediatric Patients

Duloxetine steady-state plasma concentration was comparable in pediatric patients7 to 17 years of age) and adult patients. The average steady-state duloxetine concentration was approximately 30% lower in the pediatric population relative to the adults. The model-predicted duloxetine steady state plasma concentrations in pediatric patients 7 to 17 years of age were mostly within the concentration range observed in adult patients and did not exceed the concentration range in adults.

Drug Interaction Studies

Clinical Studies: Effect of other drugs on duloxetine

Fluvoxamine:

When duloxetine 60 mg was co-administered with fluvoxamine 100 mg, a potent CYP1A2 inhibitor, to male subjects (n = 14) duloxetine AUC was increased approximately 6 fold, the Cmax was increased about 2.5 fold, and duloxetine t1/2 was increased approximately 3 fold [see Dosage and Administration (2.6) and Drug Interactions (7.1)].

Fluvoxamine in CYP2D6 poor metabolizer subjects:

Concomitant administration of duloxetine 40 mg twice daily with fluvoxamine 100 mg, a potent CYP1A2 inhibitor, to CYP2D6 poor metabolizer subjects (n = 14) resulted in a 6 fold increase in duloxetine AUC and Cmax [see Dosage and Administration (2.6) and Drug Interactions (7.1)].

Paroxetine:

Concomitant use of duloxetine (40 mg once daily) with paroxetine (20 mg once daily), a strong CYP2D6 inhibitor, increased the concentration of duloxetine AUC by about 60%, and greater degrees of inhibition are expected with higher doses of paroxetine [see Drug Interactions (7.1)].

Lorazepam:

Under steady-state conditions for duloxetine (60 mg Q 12 hours) and lorazepam (2 mg Q 12 hours), the pharmacokinetics of duloxetine were not affected by co-administration.

Temazepam:

Under steady-state conditions for duloxetine (20 mg qhs) and temazepam (30 mg qhs), the pharmacokinetics of duloxetine were not affected by co-administration.

Drugs that Affect Gastric Acidity:

Co-administration of duloxetine delayed-release capsules with aluminum- and magnesium-containing antacids (51 mEq) or duloxetine delayed-release capsules with famotidine, had no significant effect on the rate or extent of duloxetine absorption after administration of a 40 mg oral dose [see Drug Interactions (7.1)].

Clinical Studies: Effect of duloxetine on other drugs

Theophylline:

In two clinical studies the average (90% confidence interval) increase in theophylline (a CYP1A2 substrate) AUC was 7% (1% to 15%) and 20% (13% to 27%) when co-administered with duloxetine (60 mg twice daily) [see Drug Interactions (7.1)].

Desipramine:

When duloxetine was administered (at a dose of 60 mg twice daily) in conjunction with a single 50 mg dose of desipramine, a CYP2D6 substrate, the AUC of desipramine increased 3 fold [see Drug Interactions (7.1)].

Warfarin:

Under steady-state condition for warfarin (2 to 9 mg once daily) and duloxetine (60 or 120 mg once daily), the total warfarin (protein bound plus free drug) pharmacokinetics (AUCτ,ss, Cmax,ss or tmax,ss) for both R- and S-warfarin (a CYP2C9 substrate) were not altered by duloxetine [see Drug Interactions (7.1)].

In vitro Studies

Results of in vitro studies demonstrate that duloxetine does not inhibit activity of drugs metabolized by CYP3A (e.g., oral contraceptives and other steroidal agents) and drugs metabolized by CYP2C19.

Alcohol:

An in vitro study showed significant increases of duloxetine hydrochloride release from DRIZALMA SPRINKLE at 2 hours to approximately 86% and 56% of the drug release in the presence of 40% and 20% alcohol, respectively. Effect of 5% alcohol on drug release was not observed at 2 hours. There is no in vivo study conducted for the effect of alcohol on drug exposure.

13 NONCLINICAL TOXICOLOGY

13.1 Carcinogenesis, Mutagenesis, Impairment of Fertility

Carcinogenesis - Duloxetine was administered in the diet to mice and rats for 2 years.

In female mice receiving duloxetine at 140 mg/kg/day (3 times the MRHD of 120 mg/day given to children on a mg/m^2 basis), there was an increased incidence of hepatocellular adenomas and carcinomas. The no-effect dose was 50 mg/kg/day (1 times the MRHD given to children). Tumor incidence was not increased in male mice receiving duloxetine at doses up to 100 mg/kg/day (2 times the MRHD given to children).

In rats, dietary doses of duloxetine up to 27 mg/kg/day in females (1 times the MRHD given to children) and up to 36 mg/kg/day in males (1.4 times the MRHD given to children) did not increase the incidence of tumors.

Mutagenesis - Duloxetine was not mutagenic in the in vitro bacterial reverse mutation assay (Ames test) and was not clastogenic in an in vivo chromosomal aberration test in mouse bone marrow cells. Additionally, duloxetine was not genotoxic in an in vitro mammalian forward gene mutation assay in mouse lymphoma cells or in an in vitro unscheduled DNA synthesis (UDS) assay in primary rat hepatocytes, and did not induce sister chromatid exchange in Chinese hamster bone marrow in vivo.

Impairment of Fertility - Duloxetine administered orally to either male or female rats prior to and throughout mating at doses up to 45 mg/kg/day (3 times the MRHD given to adolescents on a mg/m^2 basis) did not alter mating or fertility.

14 CLINICAL STUDIES

The efficacy of duloxetine delayed-release capsules has been established in the following populations in adequate and well-controlled trials:

- Major Depressive Disorder (MDD): 4 short-term and 1 maintenance trial in adults [see Clinical Studies (14.1)].
- Generalized Anxiety Disorder (GAD): 3 short-term trials in adults, 1 maintenance trial in adults, and 1 short-term trial in pediatric patients 7 to 17 years of age [see Clinical Studies (14.2)].
- Diabetic Peripheral Neuropathic Pain (DPNP): Two 12 week trials in adults [see Clinical Studies (14.3)].
- Fibromyalgia (FM): Two trials in adults (one of 3 months duration and one of 6 months duration) [see Clinical Studies (14.4)].
- Chronic Musculoskeletal Pain: Two 12 to 13 week trials in adult patients with chronic low back pain (CLBP) and one 13 week trial in adult patients with chronic pain due to osteoarthritis [see Clinical Studies (14.5)].

Additionally, a summary of the following trials that did not demonstrate efficacy are presented below: Study FM-3 (a 16-week trial in adult patients with fibromyalgia), Study CLBP-2 (a 13-week trial in adult patients with CLBP), and Study OA-2 (a 13-week trial in adult patients with chronic pain due to OA).

14.1 Major Depressive Disorder

The efficacy of duloxetine delayed-release capsules as a treatment for MDD was established in 4 randomized, double-blind, placebo-controlled, fixed-dose trials in adult outpatients (18 to 83 years) meeting DSM-IV criteria for major depression. In Studies 1 and 2 studies, patients were randomized to duloxetine delayed-release capsules 60 mg once daily (N = 123 and N = 128, respectively) or placebo (N = 122 and N = 139, respectively) for 9 weeks; in Study 3, patients were randomized to duloxetine delayed-release capsules 20 or 40 mg twice daily (N = 86 and N = 91, respectively) or placebo (N = 89) for 8 weeks; in Study 4, patients were randomized to duloxetine delayed-release capsules 40 or 60 mg twice daily (N = 95 and N = 93, respectively) or placebo (N = 93) for 8 weeks. There is no evidence that doses greater than 60 mg/day confer additional benefits.

In all 4 trials, duloxetine delayed-release capsules demonstrated superiority over placebo as measured by improvement in the 17-item Hamilton Depression Rating Scale (HAMD-17) total score (Studies 1-4 in Table 8).

In all of these clinical trials, analyses of the relationship between treatment outcome and age, gender, and race did not suggest any differential responsiveness on the basis of these patient characteristics.

Table 8: Summary of the Primary Efficacy Results for Adult Trials in MDD

Study Number | Treatment Group | Primary Efficacy Measure: HAMD-17
Study Number | Treatment Group | Mean Baseline Score (SD) | LS Mean Change from Baseline (SE) | Placebo-subtracted Differencea (95% CI)
Study 1 | Duloxetine delayed-release (60 mg/day)b; Placebo | 21.5 (4.10); 21.1 (3.71) | -10.9 (0.70); -6.1 (0.69) | -4.9 (-6.8, -2.9); -
Study 2 | Duloxetine delayed-release (60 mg/day)b; Placebo | 20.3 (3.32); 20.5 (3.42) | -10.5 (0.71); -8.3 (0.67) | -2.2 (-4.0, -0.3); -
Study 3 | Duloxetine delayed-release (20 mg BID)b; Duloxetine delayed-release (40 mg BID)b; Placebo | 18.6 (5.85); 18.1 (4.52); 17.2 (5.11) | -7.4 (0.80); -8.6 (0.81); -5.0 (0.81) | -2.4 (-4.7, -0.2); -3.6 (-5.9, -1.4); -
Study 4 | Duloxetine delayed-release (40 mg BID)b; Duloxetine delayed-release (60 mg BID)b; Placebo | 19.9 (3.54); 20.2 (3.41); 19.9 (3.58) | -11.0 (0.49); -12.1 (0.49); -8.8 (0.50) | -2.2 (-3.6, -0.9); -3.3 (-4.7, -1.9); -

SD: standard deviation; SE: standard error; LS Mean: least-squares mean; CI: confidence interval, not adjusted for multiplicity in trials where multiple dose groups were included.

a Difference (drug minus placebo) in least-squares mean change from baseline.

b Doses statistically significantly superior to placebo.

In another trial (Study 5), 533 patients meeting DSM-IV criteria for MDD received duloxetine delayed-release capsules 60 mg once daily during an initial 12 week open-label treatment phase. Two hundred and seventy-eight patients who responded to open label treatment (defined as meeting the following criteria at weeks 10 and 12: a HAMD-17 total score ≤9, Clinical Global Impressions of Severity (CGI-S) ≤2, and not meeting the DSM-IV criteria for MDD) were randomly assigned to continuation of duloxetine delayed-release capsules at the same dose (N = 136) or to placebo (N = 142) for 6 months. Patients on duloxetine delayed-release capsules experienced a statistically significantly longer time to relapse of depression than did patients on placebo (Study 5 in Figure 1). Relapse was defined as an increase in the CGI-S score of ≥2 points compared with that obtained at week 12, as well as meeting the DSM-IV criteria for MDD at 2 consecutive visits at least 2 weeks apart, where the 2 week temporal criterion had to be satisfied at only the second visit.

Figure 1: Kaplan-Meier Estimation of Cumulative Proportion of Patients with Relapse

(MDD Study 5)

14.2 Generalized Anxiety Disorder

The efficacy of duloxetine delayed-release capsules in the treatment of generalized anxiety disorder (GAD) was established in 1 fixed-dose

The efficacy of duloxetine delayed-release capsules in the treatment of generalized anxiety disorder (GAD) was established in 1 fixed-dose randomized, double-blind, placebo-controlled trial (Study 1) and 2 flexible-dose randomized, double-blind, placebo-controlled trials Studies 2 and 3) in adult outpatients between 18 and 83 years of age meeting the DSM-IV criteria for GAD.

In 1 flexible-dose trial and in the fixed-dose trial, the starting dose was 60 mg once daily where down titration to 30 mg once daily was allowed for tolerability reasons before increasing it to 60 mg once daily. Fifteen percent of patients were down titrated. One flexible-dose study had a starting dose of 30 mg once daily for 1 week before increasing it to 60 mg once daily.

The 2 flexible-dose trials involved dose titration with duloxetine delayed-release capsules doses ranging from 60 mg once daily to 120 mg once daily (N = 168 and N = 162) compared to placebo (N = 159 and N = 161) over a 10 week treatment period. The mean dose for completers at endpoint in the flexible-dose studies was 104.75 mg/day. The fixed-dose study evaluated duloxetine delayed-release capsules doses of 60 mg once daily (N = 168) and 120 mg once daily (N = 170) compared to placebo (N = 175) over a 9 week treatment period. While a 120 mg/day dose was shown to be effective, there is no evidence that doses greater than 60 mg/day confer additional benefit.

In all 3 trials, duloxetine delayed-release capsules demonstrated superiority over placebo as measured by greater improvement in the Hamilton Anxiety Scale (HAM-A) total score (Studies 1-3 in Table 9) and by the Sheehan Disability Scale (SDS) global functional impairment score. The SDS is a composite measurement of the extent emotional symptoms disrupt patient functioning in 3 life domains: work/school, social life/leisure activities, and family life/home responsibilities.

In another trial (Study 4), 887 patients meeting DSM-IV-TR criteria for GAD received duloxetine delayed-release capsules 60 mg to 120 mg once daily during an initial 26 week open-label treatment phase. Four hundred and twenty-nine patients who responded to open-label treatment (defined as meeting the following criteria at weeks 24 and 26: a decrease from baseline HAM-A total score by at least 50% to a score no higher than 11, and a Clinical Global Impressions of Improvement [CGI-Improvement] score of 1 or 2) were randomly assigned to continuation of duloxetine delayed-release capsules at the same dose (N = 216) or to placebo (N = 213) and were observed for relapse. Of the patients randomized, 73% had been in a responder status for at least 10 weeks. Relapse was defined as an increase in CGI-Severity score at least 2 points to a score ≥4 and a MINI (Mini-International Neuropsychiatric Interview) diagnosis of GAD (excluding duration), or discontinuation due to lack of efficacy. Patients taking duloxetine delayed-release capsules experienced a statistically significantly longer time to relapse of GAD than did patients taking placebo (Study 4 in Figure 2).

Subgroup analyses did not indicate that there were any differences in treatment outcomes as a function of age or gender.

GAD Trial in Geriatric Patients

The efficacy of duloxetine delayed-release capsules in the treatment of patients ≥65 years of age with generalized anxiety disorder was established in one 10 week flexible-dose, randomized, double-blind, placebo-controlled trial (Study 5) in adults ≥65 years of age meeting the DSM-IV criteria for GAD. In this trial, the starting dose was 30 mg once daily for 2 weeks before further dose increases in 30 mg increments at treatment weeks 2, 4, and 7 up to 120 mg once daily were allowed based on investigator judgment of clinical response and tolerability. The mean dose for patients completing the 10 week acute treatment phase was 50.95 mg. Patients treated with duloxetine delayed-release capsules (N = 151) demonstrated significantly greater improvement compared with placebo (N = 140) on mean change from baseline to endpoint as measured by the Hamilton Anxiety Rating Scale total score (Study 5 in Table 9).

GAD Trial in Pediatric Patients 7 to 17 Years Old

The efficacy of duloxetine delayed-release capsules in the treatment of pediatric patients 7 to 17 years of age with generalized anxiety disorder (GAD) was established in 1 flexible-dose randomized, double-blind, placebo-controlled trial (Study 6) in pediatric outpatients with GAD (based on DSM-IV criteria).

In this trial, the starting dose was 30 mg once daily for 2 weeks. Further dose increases in 30 mg increments up to 120 mg once daily were allowed based on investigator judgment of clinical response and tolerability. The mean dose for patients completing the 10 week treatment phase was 57.6 mg/day. In this study, duloxetine delayed-release capsules (N = 135) demonstrated superiority over placebo (N = 137) from baseline to endpoint as measured by greater improvement in the Pediatric Anxiety Rating Scale (PARS) for GAD severity score (Study 6 in Table 9).

Table 9: Summary of the Primary Efficacy Results for GAD Trials

Study Number | Treatment Group | Primary Efficacy Measure
Study Number | Treatment Group | Mean Baseline Score (SD) | LS Mean Change from Baseline (SE) | Placebo-subtracted Differencea (95% CI)
Study 1; (HAM-A) | Duloxetine delayed-release (60 mg/day)b | 25.1 (7.18) | -12.8 (0.68) | -4.4 (-6.2, -2.5)
Study 1; (HAM-A) | Duloxetine delayed-release (120 mg/day)b | 25.1 (7.24) | -12.5 (0.67) | -4.1 (-5.9, -2.3)
Study 1; (HAM-A) | Placebo | 25.8 (7.66) | -8.4 (0.67) | -
Study 2 (HAM-A) | Duloxetine delayed-release (60-120 mg/day)b | 22.5 (7.44) | -8.1 (0.70) | -2.2 (-4.2, -0.3)
Study 2 (HAM-A) | Placebo | 23.5 (7.91) | -5.9 (0.70) | -
Study 3; (HAM-A) | Duloxetine delayed-release (60-120 mg/day)b | 25.8 (5.66) | -11.8 (0.69) | -2.6 (-4.5, -0.7)
Study 3; (HAM-A) | Placebo | 25.0 (5.82) | -9.2 (0.67) | -
Study 5; (Geriatric) (HAM-A) | Duloxetine delayed-release (60-120 mg/day)b | 24.6 (6.21) | -15.9 (0.63) | -4.2 (-5.9, -2.5)
Study 5; (Geriatric) (HAM-A) | Placebo | 24.5 (7.05) | -11.7 (0.67) | -
Study 6; (Pediatric) (PARS for GAD) | Duloxetine delayed-release (30-120 mg/day)b | 17.5 (1.98) | -9.7 (0.50) | -2.7 (-4.0, -1.3)
Study 6; (Pediatric) (PARS for GAD) | Placebo | 17.4 (2.24) | -7.1 (0.50) | -

SD: standard deviation; SE: standard error; LS Mean: least-squares mean; CI: confidence interval, not adjusted for multiplicity in trials where multiple dose groups were included.

a Difference (drug minus placebo) in least-squares mean change from baseline.

b Dose statistically significantly superior to placebo.

Figure 2: Kaplan-Meier Estimation of Cumulative Proportion of Patients with Relapse (GAD Study 4)

14.3 Diabetic Peripheral Neuropathic Pain in Adults

The efficacy of duloxetine delayed-release capsules for the management of neuropathic pain associated with diabetic peripheral neuropathy was established in 2 randomized, 12 week, double-blind, placebo-controlled, fixed-dose trials in adult patients having diabetic peripheral neuropathic pain for at least 6 months. Study DPNP-1 and Study DPNP-2 enrolled a total of 791 patients of whom 592 (75%) completed the studies. Patients enrolled had Type I or II diabetes mellitus with a diagnosis of painful distal symmetrical sensorimotor polyneuropathy for at least 6 months. The patients had a baseline pain score of ≥4 on an 11 point scale ranging from 0 (no pain) to 10 (worst possible pain). Patients were permitted up to 4 g of acetaminophen per day as needed for pain, in addition to duloxetine delayed-release capsules. Patients recorded their pain daily in a diary.

Both trials compared duloxetine delayed-release capsules 60 mg once daily or 60 mg twice daily with placebo. Study DPNP-1 additionally compared duloxetine delayed-release capsules 20 mg with placebo. A total of 457 patients (342 duloxetine delayed-release capsules, 115 placebo) were enrolled in Study DPNP-1 and a total of 334 patients (226 duloxetine delayed-release capsules, 108 placebo) were enrolled in Study DPNP-2. Treatment with duloxetine delayed-release capsules 60 mg one or two times a day statistically significantly improved the endpoint mean pain scores from baseline and increased the proportion of patients with at least a 50% reduction in pain scores from baseline. For various degrees of improvement in pain from baseline to study endpoint, Figures 3 and 4 show the fraction of patients achieving that degree of improvement. The figures are cumulative, so that patients whose change from baseline is, for example, 50%, are also included at every level of improvement below 50%. Patients who did not complete the study were assigned 0% improvement. Some patients experienced a decrease in pain as early as week 1, which persisted throughout the trial.

Figure 3: Percentage of Patients Achieving Various Levels of Pain Relief as Measured by 24-Hour Average Pain Severity – Study DPNP-1

Figure 4: Percentage of Patients Achieving Various Levels of Pain Relief as Measured by 24-Hour Average Pain Severity - DPNP-2

14.4 Fibromyalgia

The efficacy of duloxetine delayed-release capsules for the management of fibromyalgia in adults was established in two randomized, double-blind, placebo-controlled, fixed-dose trials in adult patients meeting the American College of Rheumatology criteria for fibromyalgia (a history of widespread pain for 3 months, and pain present at 11 or more of the 18 specific tender point sites). Study FM-1 was three months in duration and enrolled female patients only. Study FM-2 was six months in duration and enrolled male and female patients. Approximately 25% of participants had a comorbid diagnosis of MDD. Studies FM-1 and FM-2 enrolled a total of 874 patients of whom 541 (62%) completed the trials. A total of 354 patients (234 duloxetine, 120 placebo) were enrolled in Study FM-1 and a total of 520 patients (376 duloxetine, 144 placebo) were enrolled in Study FM-2 (5% male, 95% female). The patients had a baseline pain score of 6.5 on an 11-point scale ranging from 0 (no pain) to 10 (worse possible pain).

Both trials compared duloxetine 60 mg once daily or 120 mg daily (given in divided doses in Study FM-1 and as a single daily dose in Study FM-2) with placebo. Study FM-2 additionally compared duloxetine 20 mg with placebo during the initial three months of a six-month trial.

Treatment with duloxetine 60 mg or 120 mg daily statistically significantly improved the endpoint mean pain scores from baseline and increased the proportion of patients with at least a 50% reduction in pain score from baseline. Pain reduction was observed in patients both with and without comorbid MDD. However, the degree of pain reduction may be greater in patients with comorbid MDD. For various degrees of improvement in pain from baseline to study endpoint, Figures 5 and 6 show the fraction of patients achieving that degree of improvement in Studies FM-1 and FM-2, respectively. The figures are cumulative so that patients whose change from baseline is, for example, 50%, are also included at every level of improvement below 50%. Patients who did not complete the trial were assigned 0% improvement. Some patients experienced a decrease in pain as early as week 1, which persisted throughout the trial. Improvement was also demonstrated on measures of function (Fibromyalgia Impact Questionnaires) and patient global impression of change (PGI). Neither trial demonstrated a benefit of 120 mg compared to 60 mg, and a higher dosage was associated with more adverse reactions and premature discontinuations of treatment.

Figure 5: Percentage of Adult Fibromyalgia Patients Achieving Various Levels of Pain Relief at Study Endpoint as Measured by 24-Hour Average Pain Severity (Study FM-1)

Figure 6: Percentage of Adult Fibromyalgia Patients Achieving Various Levels of Pain Relief at Study Endpoint as Measured by 24-Hour Average Pain Severity (Study FM-2)

Additionally, the benefit of up-titration in non-responders to duloxetine at 60 mg/day was evaluated in a separate trial (Study FM-3). Adult patients were initially treated with duloxetine 60 mg once daily for eight weeks in open-label fashion. Subsequently, completers of this phase were randomized to double-blind treatment with duloxetine at either 60 mg once daily or 120 mg once daily. Responders were defined as patients who had at least a 30% reduction in pain score from baseline at the end of the 8-week treatment. Patients who were non-responders at 8 weeks were no more likely to meet response criteria at the end of 60 weeks of treatment if blindly titrated to duloxetine 120 mg as compared to those who were blindly continued on duloxetine 60 mg.

Additional pediatric use information is approved for Eli Lilly and Company, Inc.’s CYMBALTA (duloxetine delayed-release capsules). However, due to Eli Lilly and Company Inc.’s marketing exclusivity rights, this drug product is not labeled with that pediatric information.

14.5 Chronic Musculoskeletal Pain in Adults

Duloxetine is indicated for the management of chronic musculoskeletal pain. This has been established in trials in patients with chronic low

Duloxetine is indicated for the management of chronic musculoskeletal pain. This has been established in trials in patients with chronic low back pain and chronic pain due to osteoarthritis.

Studies in Chronic Low Back Pain

The efficacy of duloxetine delayed-release capsules in adults with chronic low back pain (Study CLBP) was assessed in two double-blind, placebo- controlled, randomized clinical trials of 13 weeks duration (Study CLBP-1 and Study CLBP-2), and one of 12 weeks duration (Study CLBP-3). Study CLBP-1 and Study CLBP-3 demonstrated efficacy of duloxetine delayed-release capsules in the treatment of chronic low back pain. Patients in all trials had no signs of radiculopathy or spinal stenosis.

Study CLBP-1: Two hundred thirty-six adult patients (N = 115 on duloxetine delayed-release capsules, N = 121 on placebo) enrolled and 182 (77%) completed 13-week treatment phase. After 7 weeks of treatment, duloxetine delayed-release capsules patients with less than 30% reduction in average daily pain and who were able to tolerate duloxetine delayed-release capsules 60 mg once daily had their dose of duloxetine delayed-release capsules, in a double-blinded fashion, increased to 120 mg once daily for the remainder of the study. Patients had a mean baseline pain rating of 6 on a numerical rating scale ranging from 0 (no pain) to 10 (worst possible pain). After 13 weeks of treatment, patients taking duloxetine delayed-release capsules 60 to 120 mg daily had a significantly greater pain reduction compared to placebo. Randomization was stratified by the patients’ baseline NSAIDs-use status. Subgroup analyses did not indicate that there were differences in treatment outcomes as a function of NSAIDs use.

Study CLBP-2: Four hundred and four patients were randomized to receive fixed doses of duloxetine delayed-release capsules daily or a matching placebo (N = 59 on duloxetine delayed-release capsules 20 mg, N = 116 on duloxetine delayed-release capsules 60 mg, N = 112 on duloxetine delayed-release capsules 120 mg, N = 117 on placebo) and 267 (66%) completed the entire 13-week study. After 13 weeks of treatment, none of the three duloxetine delayed-release capsules doses showed a statistically significant difference in pain reduction compared to placebo.

Study CLBP-3: Four hundred and one patients were randomized to receive fixed doses of duloxetine delayed-release capsules 60 mg daily or placebo (N = 198 on duloxetine delayed-release capsules, N = 203 on placebo), and 303 (76%) completed the study. Patients had a mean baseline pain rating of 6 on a numerical rating scale ranging from 0 (no pain) to 10 (worst possible pain). After 12 weeks of treatment, patients taking duloxetine delayed-release capsules 60 mg daily had significantly greater pain reduction compared to placebo.

For various degrees of improvement in pain from baseline to study endpoint, Figures 7 and 8 show the fraction of patients in Studies CLBP-1 and CLBP-3 achieving that degree of improvement. The figures are cumulative, so that patients whose change from baseline is, for example, 50%, are also included at every level of improvement below 50%. Patients who did not complete the study were assigned the value of 0% improvement.

Figure 7: Percentage of Patients Achieving Various Levels of Pain Relief as Measured by 24-Hour Average Pain Severity – Study CLBP-1

Figure 8: Percentage of Patients Achieving Various Levels of Pain Relief as Measured by 24-Hour Average Pain Severity – Study CLBP-3 Trials in Chronic Pain Due to Osteoarthritis in Adults

The efficacy of duloxetine delayed-release capsules in chronic pain due to osteoarthritis was assessed in 2 double-blind, placebo- controlled, randomized clinical trials of 13 weeks duration (Study OA-1 and Study OA-2). All patients in both trials fulfilled the ACR clinical and radiographic criteria for classification of idiopathic osteoarthritis of the knee. Randomization was stratified by the patients’ baseline NSAIDs-use status.

Patients assigned to duloxetine delayed-release capsules started treatment in both trials at a dose of 30 mg once daily for one week. After the first week, the dose of duloxetine delayed-release capsules was increased to 60 mg once daily. After 7 weeks of treatment with duloxetine delayed-release capsules 60 mg once daily, in Study OA-1 patients with sub-optimal response to treatment (<30% pain reduction) and tolerated duloxetine delayed-release capsules 60 mg once daily had their dose increased to 120 mg. However, in Study OA-2, all patients, regardless of their response to treatment after 7 weeks, were re-randomized to either continue receiving duloxetine delayed-release capsules 60 mg once daily or have their dose increased to 120 mg once daily for the remainder of the study. Patients in the placebo treatment groups in both trials received a matching placebo for the entire duration of studies. For both studies, efficacy analyses were conducted using 13-week data from the combined duloxetine delayed-release capsules 60 mg and 120 mg once daily treatment groups compared to the placebo group.

Study OA-1: Two hundred fifty-six patients (N = 128 on duloxetine delayed-release capsules, N = 128 on placebo) enrolled and 204 (80%) completed the study. Patients had a mean baseline pain rating of 6 on a numerical rating scale ranging from 0 (no pain) to 10 (worst possible pain). After 13 weeks of treatment, patients taking duloxetine delayed-release capsules had significantly greater pain reduction. Subgroup analyses did not indicate that there were differences in treatment outcomes as a function of NSAIDs use.

Study OA-2: Two hundred thirty-one patients (N = 111 on duloxetine delayed-release capsules, N = 120 on placebo) enrolled and 173 (75%) completed the study. Patients had a mean baseline pain of 6 on a numerical rating scale ranging from 0 (no pain) to 10 (worst possible pain). After 13 weeks of treatment, patients taking duloxetine delayed-release capsules did not show a significantly greater pain reduction.

In Study OA-1, for various degrees of improvement in pain from baseline to study endpoint, Figure 9 shows the fraction of patients achieving that degree of improvement. The figure is cumulative, so that patients whose change from baseline is, for example, 50%, are also included at every level of improvement below 50%. Patients who did not complete the study were assigned the value of 0% improvement.

Figure 9: Percentage of Patients Achieving Various Levels of Pain Relief as Measured by 24-Hour Average Pain Severity – Study OA-1

16 HOW SUPPLIED/STORAGE AND HANDLING

16.1 How Supplied

DRIZALMA SPRINKLE (duloxetine delayed-release capsules) are available as follows:

Features | Strengths
 | 20 mg a | 30 mg a | 40 mg a | 60 mg a
Body color | Green | White | White | Green
Cap color | Green | Blue | White | Blue
Cap imprint | RG53 | RG54 | RL85 | RG55
Body imprint | RG53 | RG54 | RL85 | RG55
Presentations and NDC Codes
Bottles of 30 | 47335-616-30 | 47335-617-30 | 47335-618-30 | 47335-619-30
Bottles of 60 | 47335-616-60 | 47335-617-60 | 47335-618-60 | 47335-619-60
Bottles of 90 | 47335-616-90 | 47335-617-90 | 47335-618-90 | 47335-619-90
Bottles of 1000 | 47335-616-10 | 47335-617-10 | 47335-618-10 | 47335-619-10

Each DRIZALMA SPRINKLE (duloxetine delayed-release capsule) contains enteric-coated pellets containing a total of 22.4 mg, 33.6 mg, 44.9 mg or 67.3 mg of duloxetine hydrochloride, USP equivalent to 20 mg, 30 mg, 40 mg or 60 mg of duloxetine, respectively.

undefined

Store at 20°C to 25°C (68°F to 77°F); excursions permitted to 15°C to 30°C (59°F to 86°F) [see USP Controlled Room Temperature].

Dispense in a tightly closed container.

For 30, 60, and 90 count bottles only: This package is child-resistant.

17 PATIENT COUNSELING INFORMATION

Advise the patient to read the FDA-approved patient labeling (Medication Guide and Instructions for Use).

Advise the patient to read the FDA-approved patient labeling (Medication Guide and Instructions for Use).Suicidal Thoughts and Behaviors - Advise patients, their families and their caregivers to look for the emergence of suicidal ideation and behavior, especially during treatment and when the dose is adjusted up or down, and instruct them to report such symptoms to their healthcare provider [see Boxed Warning, and Warnings and Precautions (5.1)].
Hepatotoxicity - Inform patients that severe liver problems, sometimes fatal, have been reported in patients treated with duloxetine delayed-release capsules. Instruct patients to talk to their healthcare provider if they develop itching, right upper belly pain, dark urine, or yellow skin/eyes while taking DRIZALMA SPRINKLE which may be signs of liver problems. Instruct patients to talk to their healthcare provider about their alcohol consumption. Use of DRIZALMA SPRINKLE with heavy alcohol intake may be associated with severe liver injury [see Warnings and Precautions (5.2)].
Alcohol - Although duloxetine delayed-release capsules does not increase the impairment of mental and motor skills caused by alcohol, use of DRIZALMA SPRINKLE concomitantly with heavy alcohol intake may be associated with severe liver injury. For this reason, DRIZALMA SPRINKLE should not be prescribed for patients with substantial alcohol use [see Warnings and Precautions (5.2) and Drug Interactions (7.1)].
Orthostatic Hypotension, Falls and Syncope - Advise patients of the risk of orthostatic hypotension, falls and syncope, especially during the period of initial use and subsequent dose escalation, and in association with the use of concomitant drugs that might potentiate the orthostatic effect of DRIZALMA SPRINKLE [see Warnings and Precautions (5.3)].
Serotonin Syndrome - Caution patients about the risk of serotonin syndrome with the concomitant use of DRIZALMA SPRINKLE and other serotonergic agents including triptans, tricyclic antidepressants, opioids, lithium, buspirone, tryptophan, amphetamines, and St. John’s Wort [see Contraindications (4), Warnings and Precautions (5.4), and Drug Interactions (7)].
Advise patients of the signs and symptoms associated with serotonin syndrome that may include mental status changes (e.g., agitation, hallucinations, delirium, and coma), autonomic instability (e.g., tachycardia, labile blood pressure, dizziness, diaphoresis, flushing, hyperthermia), neuromuscular changes (e.g., tremor, rigidity, myoclonus, hyperreflexia, incoordination), seizures, and/or gastrointestinal symptoms (e.g., nausea, vomiting, diarrhea). Caution patients to seek medical care immediately if they experience these symptoms.
Increased Risk of Bleeding - Caution patients about the concomitant use of DRIZALMA SPRINKLE and NSAIDs, aspirin, warfarin, or other drugs that affect coagulation since combined use of psychotropic drugs that interfere with serotonin reuptake and these agents has been associated with an increased risk of bleeding [see Warnings and Precautions (5.5)].
Severe Skin Reactions - Caution patients that DRIZALMA SPRINKLE may cause serious skin reactions. This may need to be treated in a hospital and may be life-threatening. Counsel patients to call their doctor right away or get emergency help if they have skin blisters, peeling rash, sores in their mouth, hives, or any other allergic reactions [see Warnings and Precautions (5.6)].
Discontinuation of Treatment - Instruct patients that discontinuation of DRIZALMA SPRINKLE may be associated with symptoms such as dizziness, headache, nausea, diarrhea, paresthesia, irritability, vomiting, insomnia, anxiety, hyperhidrosis, and fatigue, and should be advised not to alter their dosing regimen, or stop taking DRIZALMA SPRINKLE without consulting their healthcare provider [see Warnings and Precautions (5.7)].
Activation of Mania or Hypomania - Adequately screen patients with depressive symptoms for risk of bipolar disorder (e.g. family history of suicide, bipolar disorder, and depression) prior to initiating treatment with DRIZALMA SPRINKLE. Advise patients to report any signs or symptoms of a manic reaction such as greatly increased energy, severe trouble sleeping, racing thoughts, reckless behavior, talking more or faster than usual, unusually grand ideas, and excessive happiness or irritability [see Warnings and Precautions (5.8)].
Angle-Closure Glaucoma - Advise patients that taking DRIZALMA SPRINKLE can cause mild pupillary dilation, which in susceptible individuals, can lead to an episode of angle-closure glaucoma. Pre-existing glaucoma is almost always open-angle glaucoma because angle-closure glaucoma, when diagnosed, can be treated definitively with iridectomy. Open-angle glaucoma is not a risk factor for angle-closure glaucoma. Patients may wish to be examined to determine whether they are susceptible to angle-closure, and have a prophylactic procedure (e.g., iridectomy), if they are susceptible [see Warnings and Precautions (5.9)].
Seizures - Advise patients to inform their healthcare provider if they have a history of seizure disorder [see Warnings and Precautions (5.10)].
Effects on Blood Pressure - Caution patients that DRIZALMA SPRINKLE may cause an increase in blood pressure [see Warnings and Precautions (5.11)].
Concomitant Medications - Advise patients to inform their healthcare provider if they are taking, or plan to take, any prescription or over-the-counter medications, since there is a potential for interactions [see Dosage and Administration (2.10), Contraindications (4), Warnings and Precautions (5.4, 5.12), and Drug Interactions (7)].
Hyponatremia - Advise patients that hyponatremia has been reported as a result of treatment with SNRIs and SSRIs, including duloxetine delayed-release capsules. Advise patients of the signs and symptoms of hyponatremia [see Warnings and Precautions (5.13)].
Concomitant Illnesses - Advise patients to inform their healthcare provider about all of their medical conditions [see Warnings and Precautions (5.14)].
Urinary Hesitation and Retention - DRIZALMA SPRINKLE are in a class of medicines that may affect urination. Instruct patients to consult with their healthcare provider if they develop any problems with urine flow [see Warnings and Precautions (5.15)].
Sexual Dysfunction - Advise patients that use of DRIZALMA SPRINKLE may cause symptoms of sexual dysfunction in both male and female patients. Inform patients that they should discuss any changes in sexual function and potential management strategies with their healthcare provider [see Warnings and Precautions (516)].
Pregnancy
• Advise pregnant women to notify their healthcare provider if they become pregnant or intend to become pregnant during treatment with DRIZALMA SPRINKLE.
• Advise patients that DRIZALMA SPRINKLE may increase the risk of neonatal complications requiring prolonged hospitalization, respiratory support and tube feeding.
• Advise pregnant women that there is a risk of relapse with discontinuation of antidepressants.
• Advise patients that there is a pregnancy exposure registry that monitors pregnancy outcomes in women exposed to duloxetine during pregnancy [see Use in Specific Populations (8.1)].
Lactation- Advise breastfeeding women using DRIZALMA SPRINKLE to monitor infants for sedation, poor feeding and poor weight gain and to seek medical care if they notice these signs [see Use in Specific Populations (8.2)].
Interference with Psychomotor Performance - DRIZALMA SPRINKLE may be associated with sedation and dizziness. Therefore, caution patients about operating hazardous machinery including automobiles, until they are reasonably certain that DRIZALMA SPRINKLE therapy does not affect their ability to engage in such activities.

This product, or its use, may be covered by one or more US patents, including US Patent No. 9,839,626 in addition to others including patents pending.
DRIZALMA SPRINKLE is a trademark of Sun Pharmaceutical Industries Limited.
All other trademarks are the property of their respective owners.
Manufactured by:
Sun Pharmaceutical Industries Limited,
Mohali, INDIA
Distributed by:
Sun Pharmaceutical Industries, Inc.
Cranbury, NJ 08512

FDA-13

Medication Guide

DRIZALMA SPRINKLE™ (dri zal' mah)

(duloxetine delayed-release capsules)

What is the most important information I should know about DRIZALMA SPRINKLE?

DRIZALMA SPRINKLE may cause serious side effects, including:

•Increased risk of suicidal thoughts or actions. DRIZALMA SPRINKLE and other antidepressant medicines may increase suicidal thoughts and actions in some people 24 years of age and younger, especially within the first few months of treatment or when the dose is changed. •Depression and other serious mental illnesses are the most important causes of suicidal thoughts or actions.How can I watch for and try to prevent suicidal thoughts and actions? oPay close attention to any changes in mood, behavior, actions, thoughts, or feelings, especially sudden changes. This is very important when an antidepressant medicine is started or when the dose is changed.oCall your healthcare provider right away to report new or sudden changes in mood, behavior, thoughts, or feelings.oKeep all follow-up visits with your healthcare provider as scheduled. Call your healthcare provider between visits as needed, especially if you have concerns about symptoms.Call your healthcare provider or get emergency help right away if you or your family member have any of the following symptoms, especially if they are new, worse, or worry you:

•attempts to commit suicide

•acting on dangerous impulses

•acting aggressive, being angry, or violent

•thoughts about suicide or dying

•new or worse depression

•new or worse anxiety

•panic attacks

•feeling very agitated or restless

•new or worse irritability

•trouble sleeping

•an extreme increase in activity or talking (mania)

•other unusual changes in behavior or mood

What is DRIZALMA SPRINKLE?

DRIZALMA SPRINKLE is prescription medicine used to treat:

•A certain type of depression called Major Depressive Disorder (MDD) in adults•Generalized Anxiety Disorder (GAD) in adults and children 7 years of age and older•Diabetic Peripheral Neuropathic Pain (DPNP) in adults•Fibromyalgia (FM) in adults•Chronic Musculoskeletal Pain in adultsIt is not known if DRIZALMA SPRINKLE is safe and effective for use to treat GAD in children less than 7 years of age.

It is not known if DRIZALMA SPRINKLE is safe and effective for use to treat MDD, DPNP, and Chronic Musculoskeletal Pain in children.

Do not take DRIZALMA SPRINKLE if you:

•take a Monoamine Oxidase Inhibitor (MAOI)•have stopped taking an MAOI in the last 14 days•are being treated with the antibiotic linezolid or intravenous methylene blue

Ask your healthcare provider or pharmacist if you are not sure if you take an MAOI, including the antibiotic linezolid or intravenous methylene blue.

Do not start taking an MAOI for a least 5 days after you stop treatment with DRIZALMA SPRINKLE.

Before taking DRIZALMA SPRINKLE, tell your healthcare provider about all your medical conditions, including if you:

•have or have a family history of suicide, bipolar disorder, depression, mania or hypomania•have liver or kidney problems•drink alcohol•have or had had bleeding problems•have glaucoma (high pressure in the eye)•have or have had seizures (convulsions)•have high or low blood pressure•have diabetes or high blood sugar•have or have had heart problems or stroke•have low sodium levels in your blood•have problems urinating (hesitation) or emptying your bladder (urinary retention)•are pregnant or plan to become pregnant. DRIZALMA SPRINKLE may harm your unborn baby. Talk to your healthcare provider about the risks to you and your unborn baby if you take DRIZALMA SPRINKLE during pregnancy.•Tell your healthcare provider right away if you become pregnant or think you are pregnant during treatment with DRIZALMA SPRINKLE.•If you become pregnant during treatment with DRIZALMA SPRINKLE, talk to your healthcare provider about registering with the National Pregnancy Registry for Antidepressants. You can register by calling 1-844-405-6185 or by visiting online at https://womensmentalhealth.org/clinical-and-research-programs/pregnancyregistry/antidepressants/•are breastfeeding or plan to breastfeed. DRIZALMA SPRINKLE passes into your breast milk and may harm your baby. Talk to your healthcare provider about the best way to feed your baby during treatment with DRIZALMA SPRINKLE.

Tell your healthcare provider about all the medicines you take, including prescription and over-the-counter medicines, vitamins, and herbal supplements.

DRIZALMA SPRINKLE and other medicines may affect each other causing possible serious side effects. DRIZALMA SPRINKLE may affect the way other medicines work and other medicines may affect the way DRIZALMA SPRINKLE works.

What should I tell my healthcare provider before taking DRIZALMA SPRINKLE? Ask if you are not sure:
• medicines to treat migraine headaches known as triptans
• tricyclic antidepressants
• lithium
• tramadol, fentanyl, meperidine, methadone, or other opioids
• tryptophan
• buspirone
• amphetamines
• St. John’s Wort
• other medicines containing desvenlafaxine or venlafaxine
• medicines that can affect blood clotting such as aspirin, nonsteroidal anti-inflammatory drugs (NSAIDs), warfarin

Ask your healthcare provider if you are not sure if you are taking any of these medicines. Your healthcare provider can tell you if it is safe to take DRIZALMA SPRINKLE with your other medicines.

Do not start or stop any other medicines during treatment with TREATMENT without talking to your healthcare provider first. Stopping DRIZALMA SPRINKLE suddenly may cause you to have serious side effects. See, “What are the possible side effects of DRIZALMA SPRINKLE?”

Know the medicines you take. Keep a list of them to show to your healthcare provider and pharmacist when you get a new medicine.

How should I take DRIZALMA SPRINKLE?

•Take DRIZALMA SPRINKLE exactly as your healthcare provider tells you to take it. Do not change your dose or stop taking DRIZALMA SPRINKLE without talking to your healthcare provider.•Your healthcare provider may need to change the dose of DRIZALMA SPRINKLE until it is the right dose for you.•Take DRIZALMA SPRINKLE with or without food.•Swallow DRIZALMA SPRINKLE whole. Do not chew or crush DRIZALMA SPRINKLE.•If you have trouble swallowing DRIZALMA SPRINKLE whole, you can open the capsule and take the contents with applesauce. See the Instructions for Use at the end of this Medication Guide for instructions on how to take DRIZALMA SPRINKLE with applesauce.•See the Instructions for Use at the end of this Medication Guide for instructions on how to mix and give DRIZALMA SPRINKLE through a nasogastric (NG) tube.•If you miss a dose of DRIZALMA SPRINKLE, take the missed dose as soon as you remember. If it is almost time for the next dose, skip the missed dose and take your next dose at the regular time. Do nottake 2 doses of DRIZALMA SPRINKLE at the same time.

If you take too much DRIZALMA SPRINKLE, call your healthcare provider or poison control center at 1800-222-1222 right away, or go to the nearest hospital emergency room.

What are the possible side effects of DRIZALMA SPRINKLE?

DRIZALMA SPRINKLE may cause serious side effects, including:

•See, “What is the most important information I should know about DRIZALMA SPRINKLE?” •Liver problems. DRIZALMA SPRINKLE may cause severe liver problems that may cause death. Tell your healthcare provider right away if you develop any of the following symptoms of severe liver problems:•Decreased in blood pressure (orthostatic hypotension). You may feel lightheaded or faint when you rise too quickly from a sitting or lying position, especially when you start or restart treatment or when the dose is changed.•Falls and fainting. DRIZALMA SPRINKLE may cause you to feel sleepy or dizzy, may cause a decrease in your blood pressure when you rise to quickly from a sitting or lying position, and can slow your thinking and motor skills which may lead to falls that have caused fractures or other serious injuries.•Serotonin syndrome. A potentially life-threatening problem called serotonin syndrome can happen when you take DRIZALMA SPRINKLE with certain other medicines. See, “Who should not take DRIZALMA SPRINKLE?” Call your healthcare provider or go to the nearest hospital emergency room right away if you have any of the following signs and symptoms of serotonin syndrome:•Abnormal bleeding. Taking DRIZALMA SPRINKLE with aspirin, non-steroidal anti-inflammatory drugs (NSAIDs), or blood thinners may add to this risk. Tell your healthcare provider right away about any unusual bleeding or bruising.•Severe skin reactions. DRIZALMA SPRINKLE may cause serious skin reactions that may need to be treated in a hospital and may be life-threating. Stop taking DRIZALMA SPRINKLE and call your healthcare provider or get emergency help right away if you develop skin blisters, peeling rash, sores in the mouth, hives or any other allergic reactions during treatment with DRIZALMA SPRINKLE.

•Discontinuation syndrome. Suddenly stopping DRIZALMA SPRINKLE when you take higher doses may cause you to have serious side effects. Your healthcare provider may want to decrease your dose slowly. Symptoms may include:•Manic episodes. Manic episodes may happen in people with bipolar disorder who take DRIZALMA SPRINKLE. Symptoms may include:•Eye problems (angle-closure glaucoma). DRIZALMA SPRINKLE may cause a type of eye problem called angle-closure glaucoma in people with certain other eye conditions. You may want to undergo an eye examination to see if you are at risk and receive preventative treatment if you are. Call your healthcare provider if you have eye pain, changes in your vision, or swelling or redness in or around the eye. Seizures (convulsions). •Increases in blood pressure. Your healthcare provider should check your blood pressure regularly during treatment with DRIZALMA SPRINKLE. If you have high blood pressure, it should be controlled before you start treatment with DRIZALMA SPRINKLE.•Low sodium levels in your blood (hyponatremia). Low sodium levels can happen during treatment with DRIZALMA SPRINKLE. Low sodium levels in your blood may be serious and may cause death. Elderly people may be at greater risk for this. Signs and Symptoms of low sodium levels in your blood may include:oheadacheodifficulty concentratingomemory changesoconfusionoweakness and unsteadiness on your feet which can lead to fallsIn severe or more sudden cases, signs and symptoms include:ohallucinations (seeing or hearing things that are not real)ofaintingoseizuresocomaorespiratory arrestodeath•Problems with urination. DRIZALMA SPRINKLE may cause you to have problems with urination including decreased urine flow and being unable to pass any urine. Tell your healthcare provider if you develop any problems with urine flow during treatment with DRIZALMA SPRINKLE.•Sexual problems (dysfunction).Taking serotonin and norepinephrine reuptake inhibitors (SNRIs), including DRIZALMA SPRINKLE, may cause sexual problems.Symptoms in males may include:oDelayed ejaculation or inability to have an ejaculationoDecreased sex driveoProblems getting or keeping an erectionSymptoms in females may include:oDecreased sex driveoDelayed orgasm or inability to have an orgasmTalk to your healthcare provider if you develop any changes in your sexual function or if you have any questions or concerns about sexual problems during treatment with DRIZALMA SPRINKLE. There may be treatments your healthcare provider can suggest.

Your healthcare provider may tell you to stop taking DRIZALMA SPRINKLE if you develop serious side effects during treatment with DRIZALMA SPRINKLE.

The most common side effects of DRIZALMA SPRINKLE in adults include:

The most common side effects of DRIZALMA SPRINKLE in children include:

Height and weight changes in children and adolescents may happen during treatment with DRIZALMA SPRINKLE. Your healthcare provider should check your child’s or adolescent’s height and weight during treatment with DRIZALMA SPRINKLE.

These are not all the possible side effects of DRIZALMA SPRINKLE.

Call your doctor for medical advice about side effects. You may report side effects to FDA at 1-800-FDA-1088.

How should I store DRIZALMA SPRINKLE?

•Store DRIZALMA SPRINKLE at room temperature between 68°F to 77°F (20°C to 25°C).•Store DRIZALMA SPRINKLE in a tightly closed container.Keep DRIZALMA SPRINKLE and all medicines out of the reach of children.

General information about the safe and effective use of DRIZALMA SPRINKLE.

Medicines are sometimes prescribed for purposes other than those listed in a Medication Guide. Do not use DRIZALMA SPRINKLE for a condition for which it was not prescribed. Do not give DRIZALMA SPRINKLE to other people, even if they have the same symptoms that you have. It may harm them. You may ask your healthcare provider or pharmacist for information about DRIZALMA SPRINKLE that is written for healthcare professionals.

What are the ingredients in DRIZALMA SPRINKLE?

Active ingredient: duloxetine hydrochloride

Inactive ingredients: ascorbic acid, hypromellose, hypromellose phthalate, polyethylene glycol, starch, sucrose, sugar spheres, talc, titanium dioxide, and triethyl citrate.

The capsule shell ingredients for 20 mg strength are D&C Yellow 10, FD &C Blue 1, FD &C Red 40, gelatin, sodium lauryl sulfate and titanium dioxide. The capsule shell ingredients for 30 mg strength are FD &C Blue 1, FD &C Red 40 and FD &C Red 3 (present in cap), gelatin, sodium lauryl sulfate and titanium dioxide. The capsule shell ingredients for 40 mg strength are gelatin, sodium lauryl sulfate and titanium dioxide. The capsule shell ingredients for 60 mg strength are D&C Yellow 10 (present in body), FD &C Blue 1, FD &C Red 40, FD &C Red 3 (present in cap), gelatin, sodium lauryl sulfate and titanium dioxide.The imprinting ink for 20 mg, 30 mg, 40 mg, and 60 mg strength capsules was made of ammonia solution, black iron oxide, butyl alcohol, dehydrated alcohol, isopropyl alcohol, potassium hydroxide, propylene glycol and shellac.Manufactured by:Sun Pharmaceutical Industries Limited,Mohali, INDIADistributed by:Sun Pharmaceutical Industries, Inc.Cranbury, NJ 08512FDA-05For more information call Sun Pharmaceutical Industries, Inc. at 1-800-818-4555.

This Medication Guide has been approved by the U.S. Food and Drug Administration. Revised: August/2023

Instructions for Use

DRIZALMA SPRINKLE (dri zal' mah)

(duloxetine delayed-release capsules)

Taking DRIZALMA SPRINKLE with applesauce:

1.Carefully open the DRIZALMA SPRINKLE capsule.2.Sprinkle the pellets from the capsules on 1 tablespoonful of applesauce.3.Swallow the applesauce and pellets mixture right away. Do not chew the pellets.4.Do not save the applesauce and pellets mixture for later use. Throw away any remaining applesauce and pellets mixture.

Giving DRIZALMA SPRINKLE through a nasogastric tube (NG tube) 12 French or larger as prescribed by your healthcare provider:

For people who have a NG tube in place, DRIZALMA SPRINKLE may be given as follows:

•Remove the plunger from a 60 mL catheter tipped syringe.•Carefully open the DRIZALMA SPRINKLE capsule and empty the pellets into the catheter tipped syringe barrel.•Add 50 mL of water to the pellets that are inside of the catheter tipped syringe barrel. Do not use other liquids.•Replace the plunger and gently shake the syringe well for approximately 10 seconds.•Insert the catheter tipped syringe to a NG tube (≥12 French).•Give the mixture right away through the NG tube into the stomach. Do not save the mixture for later use.•After giving the mixture, the NG tube should be flushed with 15 mL of additional water.

How should I store DRIZALMA SPRINKLE?

•Store DRIZALMA SPRINKLE at room temperature between 68°F to 77°F (20°C to 25°C).•Store DRIZALMA SPRINKLE in a tightly closed container. Keep DRIZALMA SPRINKLE and all medicines out of the reach of children.Manufactured by:Sun Pharmaceutical Industries Limited,Mohali, INDIADistributed by:Sun Pharmaceutical Industries, Inc.Cranbury, NJ 08512FDA-02

This Instructions for Use has been approved by the U.S. Food and Drug Administration. Issued: July/2021

PACKAGE/LABEL PRINCIPAL DISPLAY PANEL

NDC 47335-616-30
Drizalma Sprinkle™
(duloxetine delayed-release capsules)
20 mg
30 Capsules
Rx only
SUN PHARMA

PACKAGE/LABEL PRINCIPAL DISPLAY PANEL

NDC 47335-617-30
Drizalma Sprinkle™
(duloxetine delayed-release capsules)
30 mg
30 Capsules
Rx only
SUN PHARMA

PACKAGE/LABEL PRINCIPAL DISPLAY PANEL

NDC 47335-618-30
Drizalma Sprinkle™
(duloxetine delayed-release capsules)
40 mg
30 Capsules
Rx only
SUN PHARMA

PACKAGE/LABEL PRINCIPAL DISPLAY PANEL

NDC 47335-619-30
Drizalma Sprinkle™
(duloxetine delayed-release capsules)
60 mg
30 Capsules
Rx only